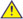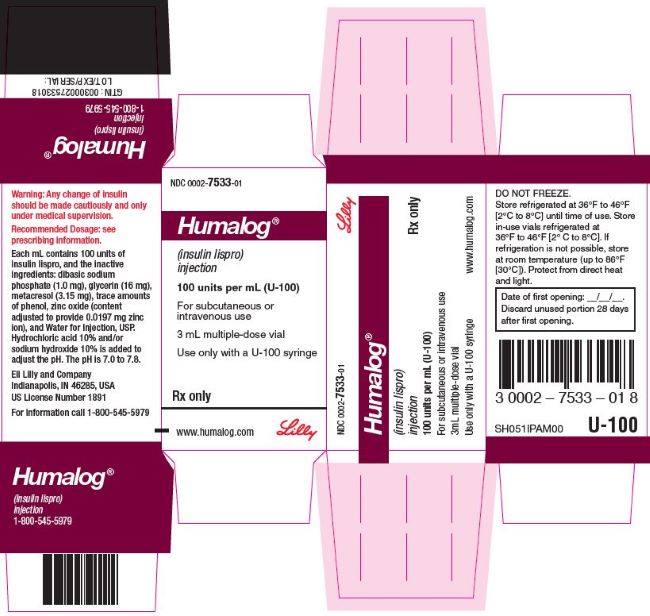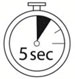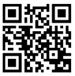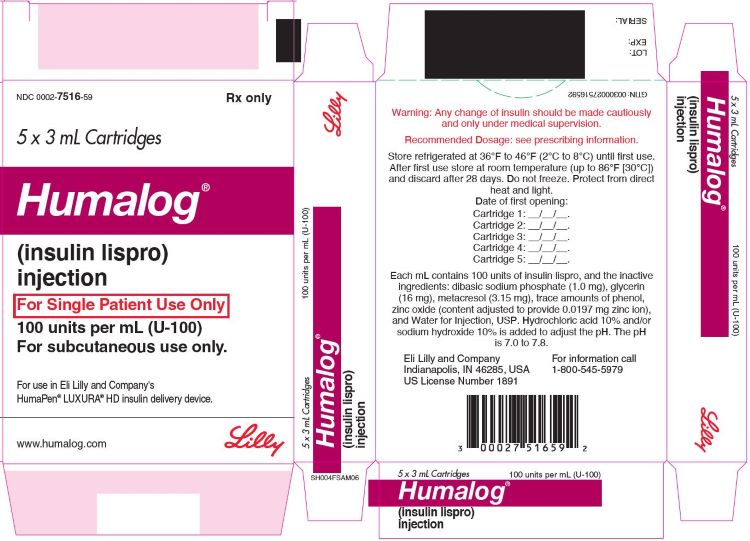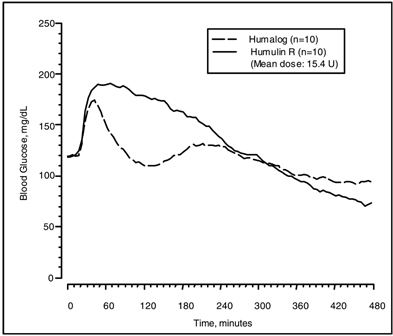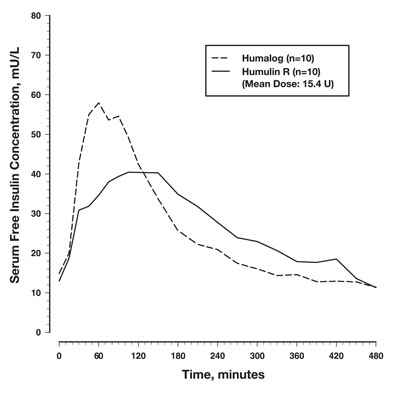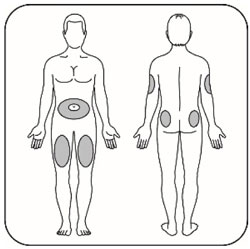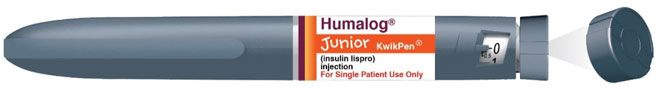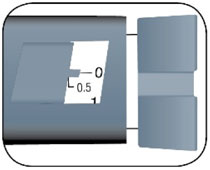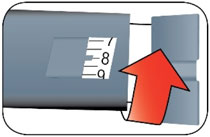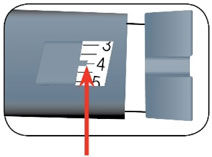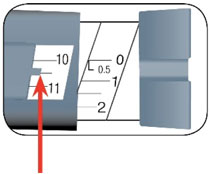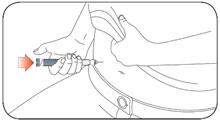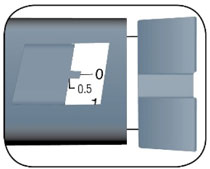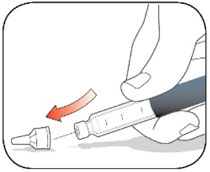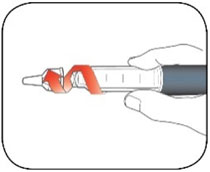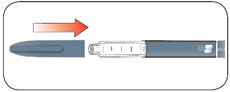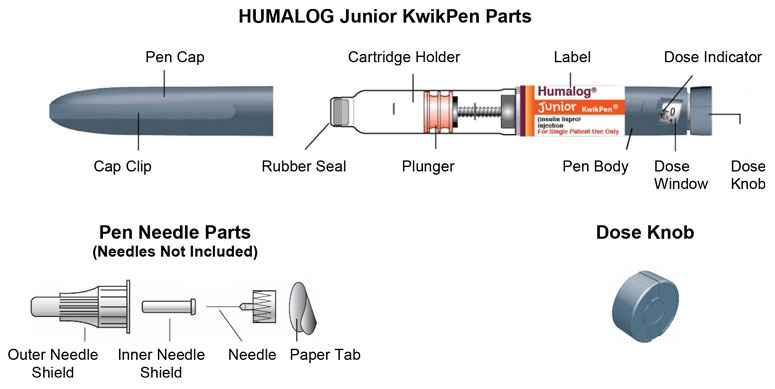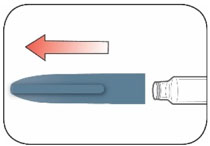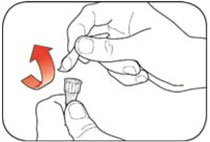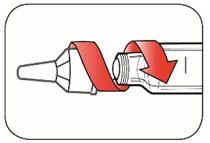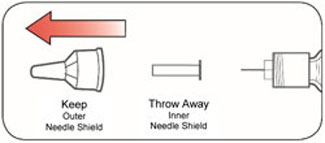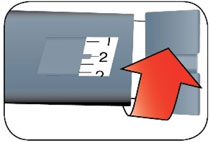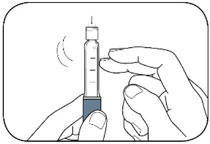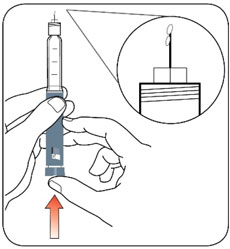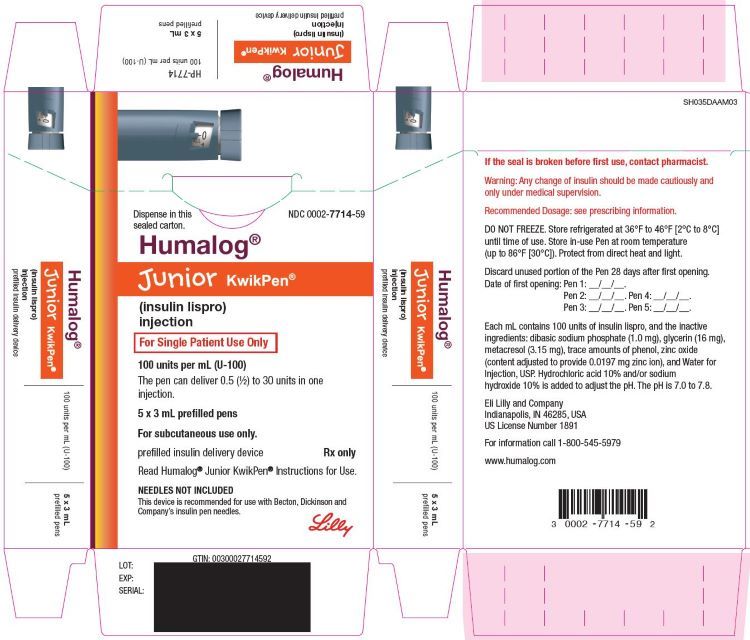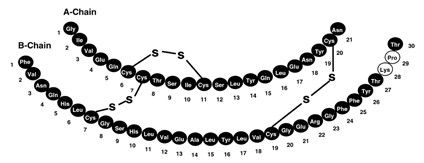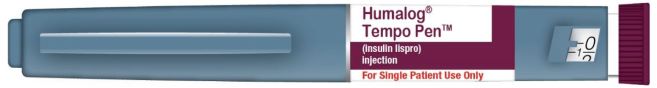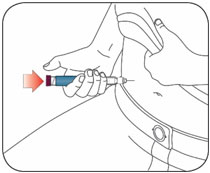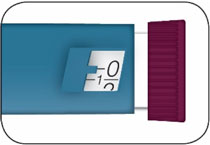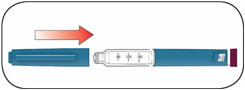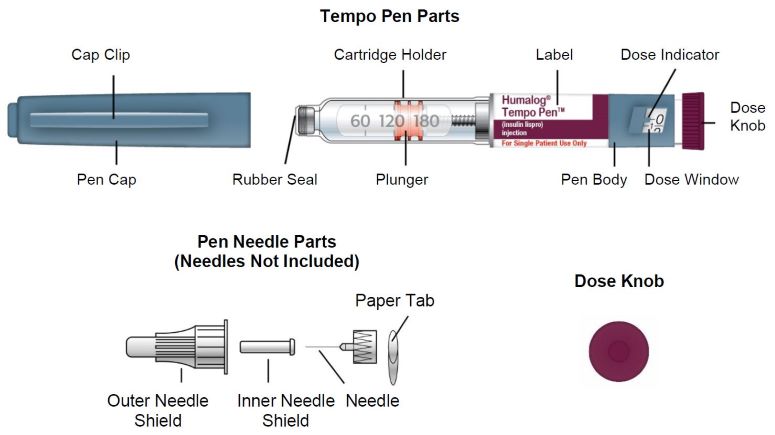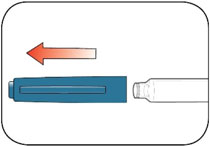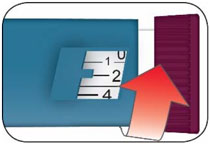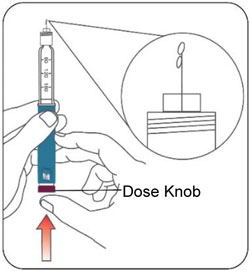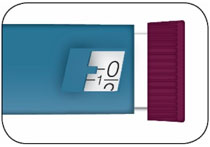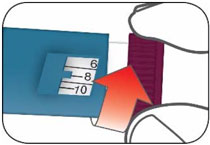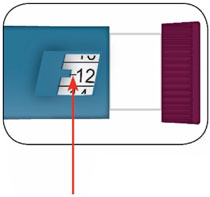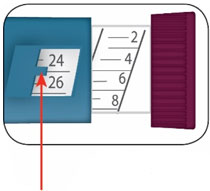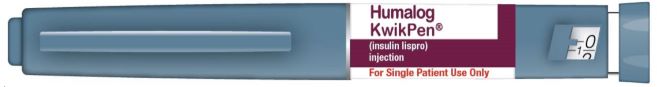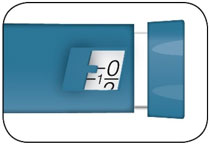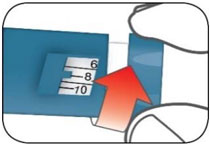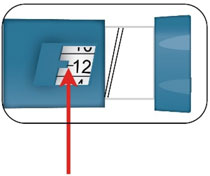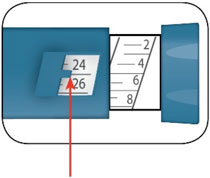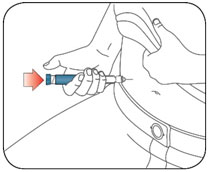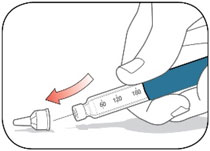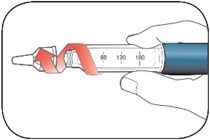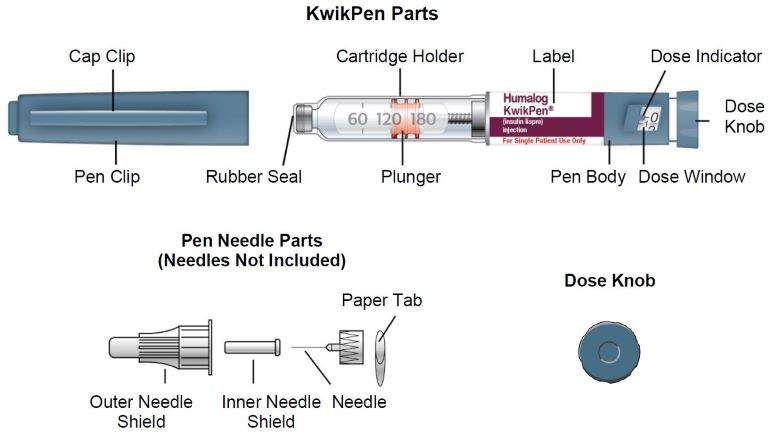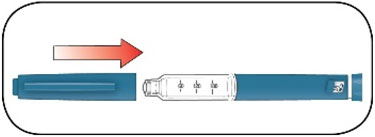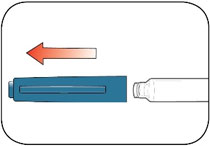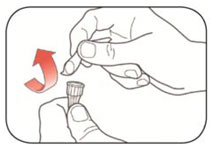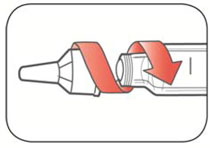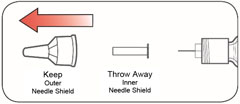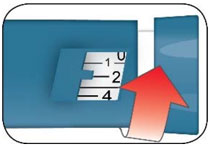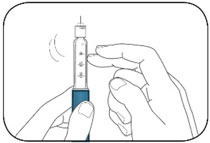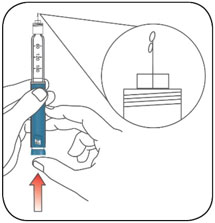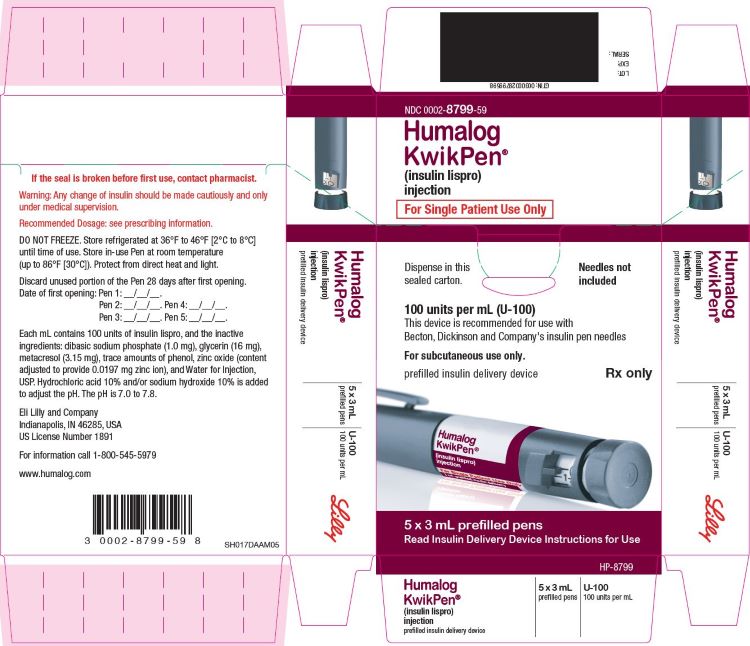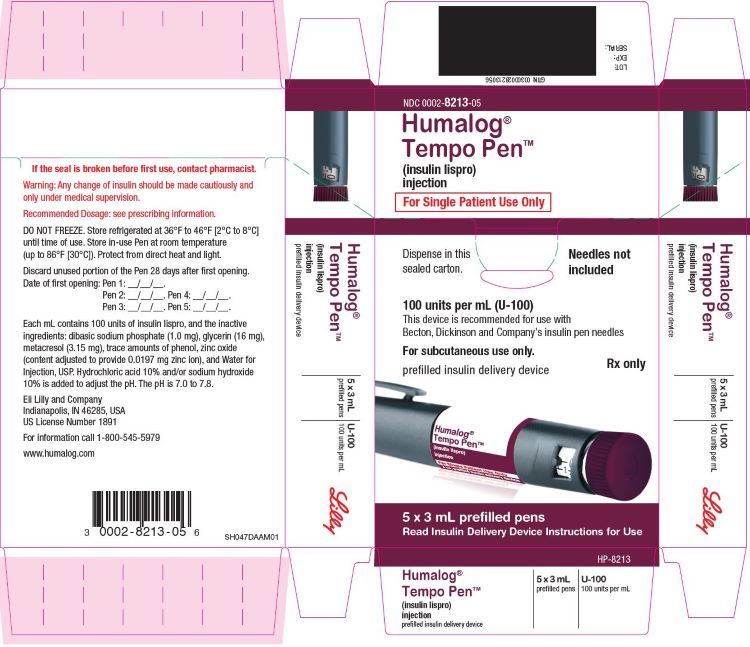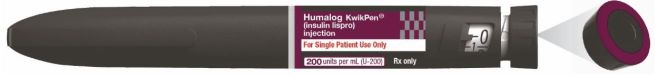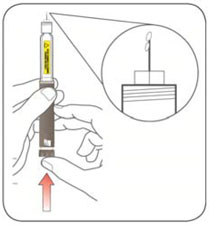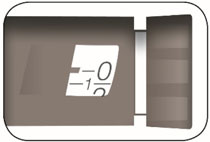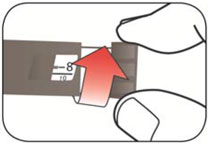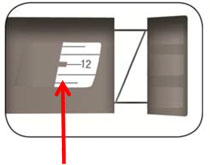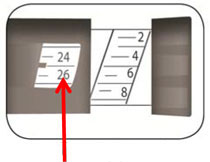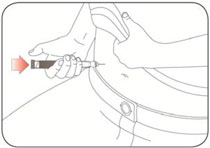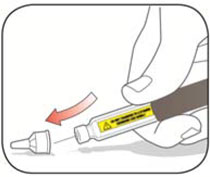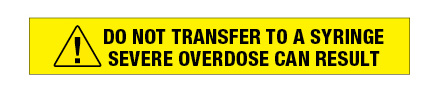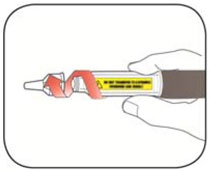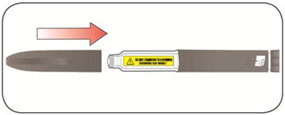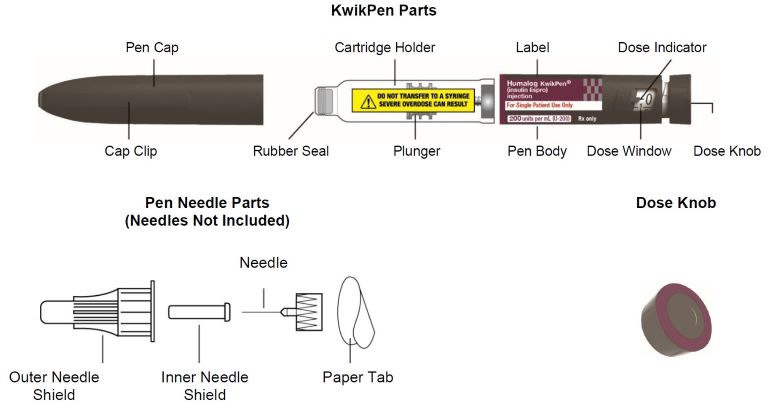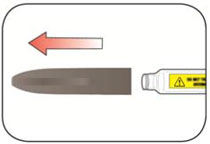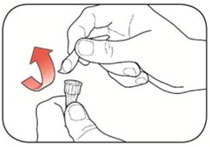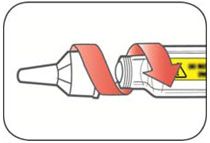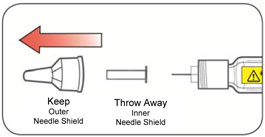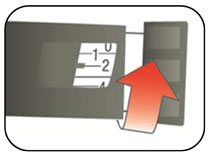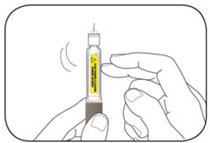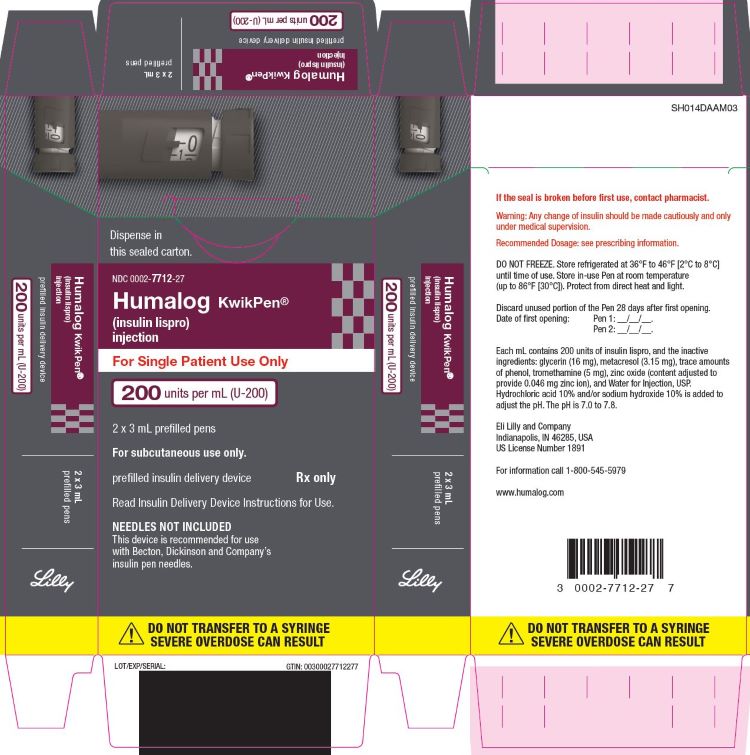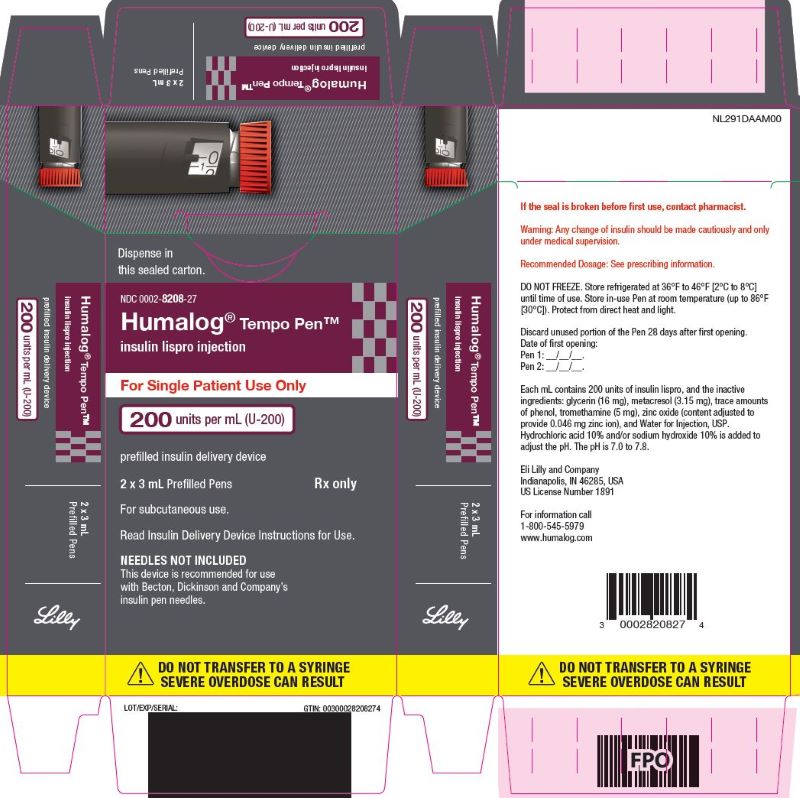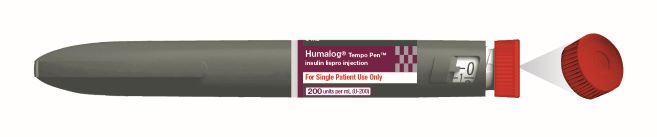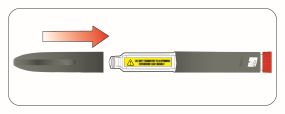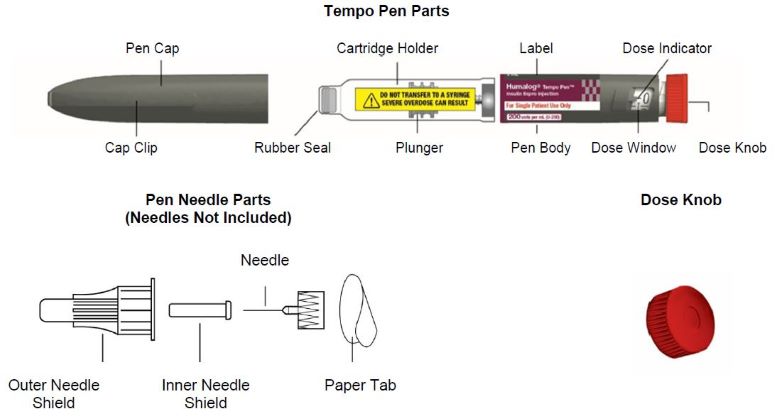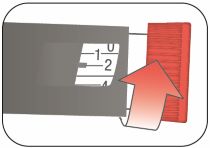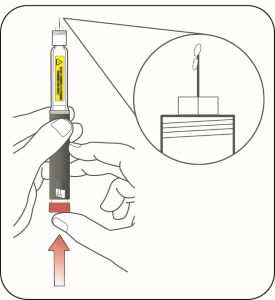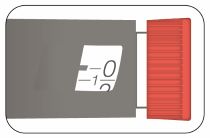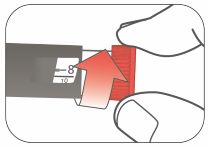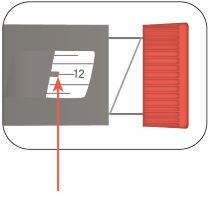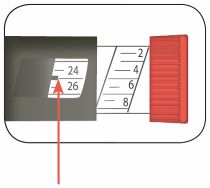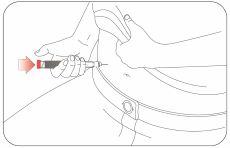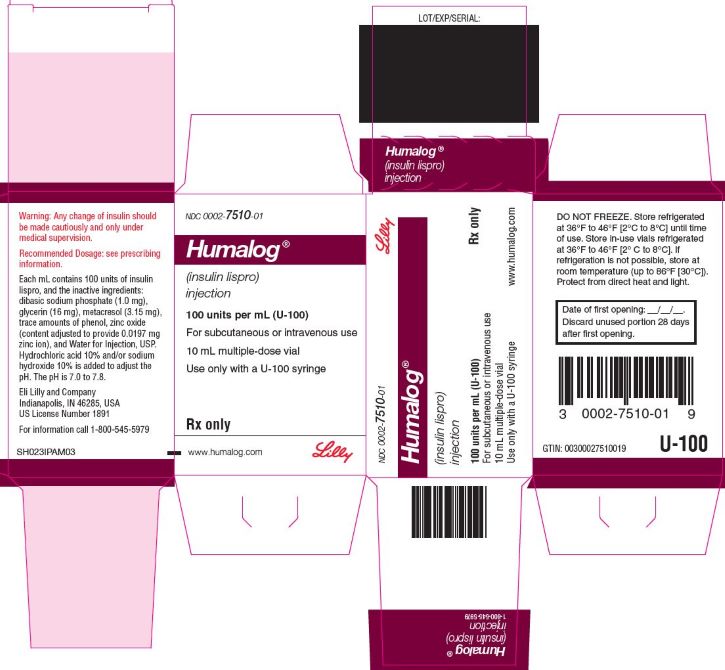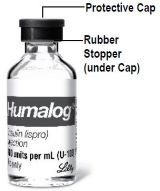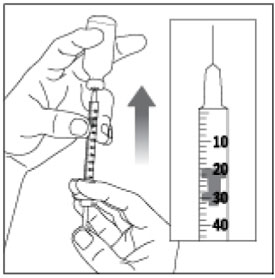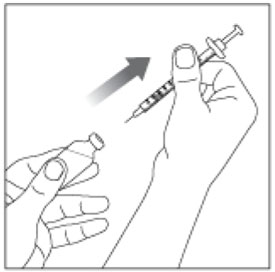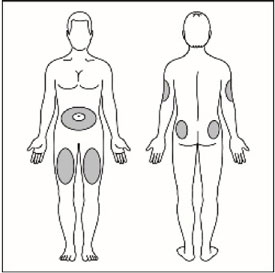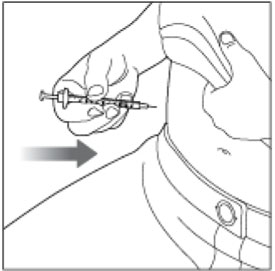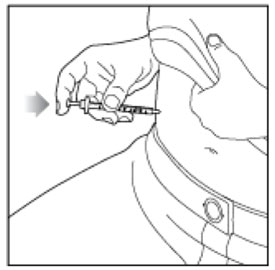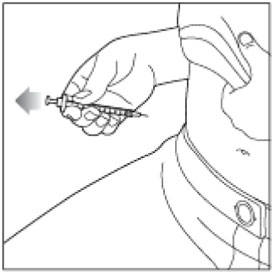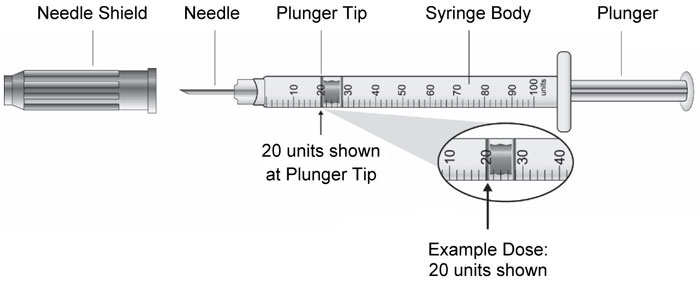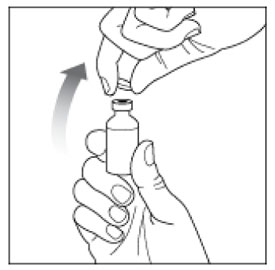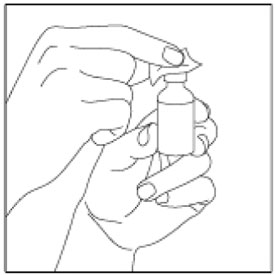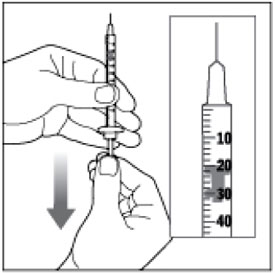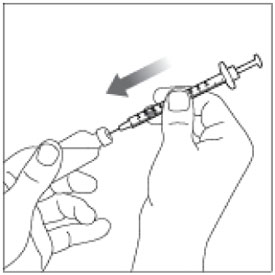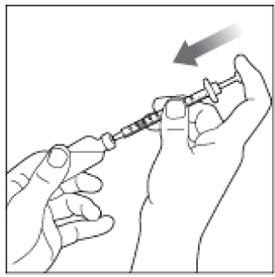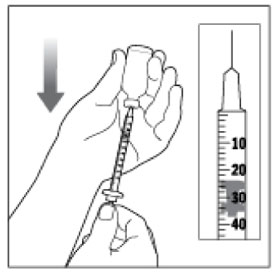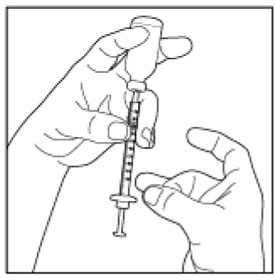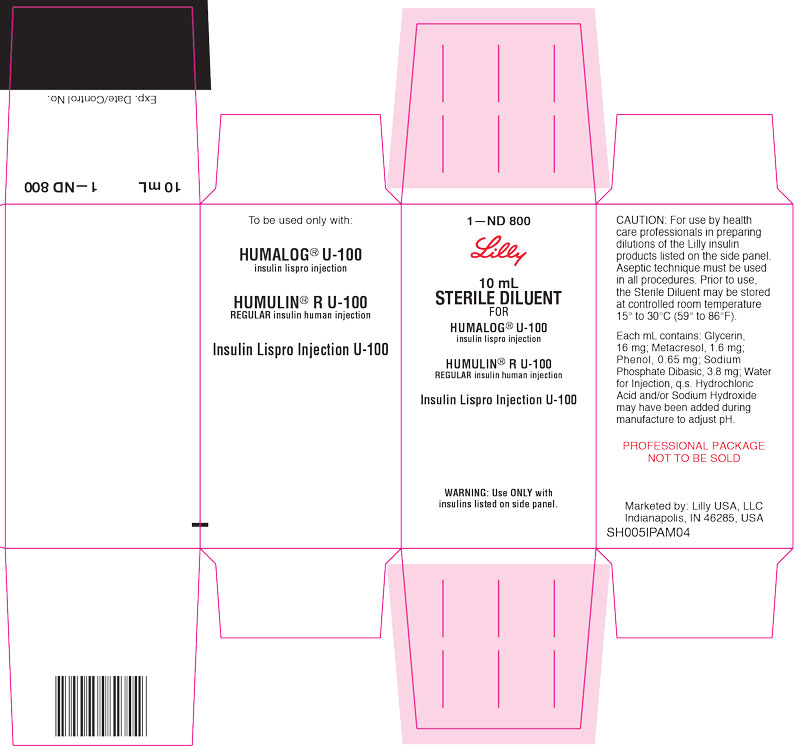 DRUG LABEL: Humalog
NDC: 0002-7510 | Form: INJECTION, SOLUTION
Manufacturer: Eli Lilly and Company
Category: prescription | Type: HUMAN PRESCRIPTION DRUG LABEL
Date: 20250617

ACTIVE INGREDIENTS: Insulin lispro 100 [iU]/1 mL
INACTIVE INGREDIENTS: Sodium Phosphate, Dibasic, Unspecified Form 1.0 mg/1 mL; Glycerin 16 mg/1 mL; Metacresol 3.15 mg/1 mL; Phenol; Zinc .0197 mg/1 mL; Water; Hydrochloric acid; Sodium hydroxide

HIGHLIGHTS OF PRESCRIBING INFORMATION

These highlights do not include all the information needed to use HUMALOG safely and effectively. See full prescribing information for HUMALOG.
HUMALOG (insulin lispro) injection, for subcutaneous or intravenous use
Initial U.S. Approval: 1996

RECENT MAJOR CHANGES

Dosage and Administration (2.2) | 05/2025

1 INDICATIONS AND USAGE

HUMALOG is a rapid acting human insulin analog indicated to improve glycemic control in adult and pediatric patients with diabetes mellitus. (1)

2 DOSAGE AND ADMINISTRATION

- See Full Prescribing Information for important administration instructions. (2.1, 2.2, 2.3, 2.4)
- Subcutaneous injection (2.2):
  - Administer HUMALOG® U-100 or U-200 by subcutaneous injection into the abdominal wall, thigh, upper arm, or buttocks within 15 minutes before a meal or immediately after a meal.
  - Rotate injection sites to reduce risk of lipodystrophy and localized cutaneous amyloidosis.
- Continuous subcutaneous infusion (Insulin Pump) (2.2):
  - Refer to the insulin infusion pump user manual to see if HUMALOG can be used. Use in accordance with the insulin pump instructions for use.
  - Administer HUMALOG U-100 by continuous subcutaneous infusion using an insulin pump in a region recommended in the instructions from the pump manufacturer.
  - Rotate infusion sites to reduce risk of lipodystrophy and localized cutaneous amyloidosis.
  - DO NOT administer HUMALOG U-200 by continuous subcutaneous infusion.
- Intravenous Infusion (2.2):
  - Administer HUMALOG U-100 by intravenous infusion ONLY after dilution and under medical supervision. DO NOT administer HUMALOG U-200 by intravenous infusion.
- The dosage of HUMALOG must be individualized based on the route of administration and the individual's metabolic needs, blood glucose monitoring results and glycemic control goal. (2.3)
- Do not perform dose conversion when using the HUMALOG U-100 or U-200 prefilled pens. The dose window shows the number of insulin units to be delivered and no conversion is needed. (2.1, 2.3)
- Do not mix HUMALOG U-200 with any other insulin. (2.4)

3 DOSAGE FORMS AND STRENGTHS

Injection: 100 units/mL (U-100) is available as: (3)

- 10 mL multiple-dose vial
- 3 mL multiple-dose vial
- 3 mL single-patient-use KwikPen® prefilled pen
- 3 mL single-patient-use Tempo Pen™ prefilled pen
- 3 mL single-patient-use Junior KwikPen® prefilled pen
- 3 mL single-patient-use cartridges

Injection: 200 units/mL (U-200) is available as: (3)

- 3 mL single-patient-use KwikPen® prefilled pen
- 3 mL single-patient-use Tempo PenTM prefilled pen

4 CONTRAINDICATIONS

- Do not use during episodes of hypoglycemia. (4)
- Do not use in patients with hypersensitivity to insulin lispro or any of the excipients in HUMALOG. (4)

5 WARNINGS AND PRECAUTIONS

- Never share a HUMALOG prefilled pen, cartridge, reusable pen compatible with Lilly 3 mL cartridges, or syringe between patients, even if the needle is changed. (5.1)
- Hyperglycemia or Hypoglycemia with Changes in Insulin Regimen: Make changes to a patient's insulin regimen (e.g., insulin strength, manufacturer, type, injection site or method of administration) under close medical supervision with increased frequency of blood glucose monitoring. (5.2)
- Hypoglycemia: May be life-threatening. Monitor blood glucose and increase monitoring frequency with changes to insulin dosage, use of glucose lowering medications, meal pattern, physical activity; in patients with renal or hepatic impairment; and in patients with hypoglycemia unawareness. (5.3, 7, 8.6, 8.7)
- Hypoglycemia Due to Medication Errors: Accidental mix-ups between insulin products can occur. Instruct patients to check insulin labels before injection. Do not transfer HUMALOG U-200 from the HUMALOG prefilled pen to a syringe as overdosage and severe hypoglycemia can result. (5.4)
- Hypersensitivity Reactions: May be life-threatening. Discontinue HUMALOG, monitor and treat if indicated. (5.5)
- Hypokalemia: May be life-threatening. Monitor potassium levels in patients at risk of hypokalemia and treat if indicated. (5.6)
- Fluid Retention and Heart Failure with Concomitant Use of Thiazolidinediones (TZDs): Observe for signs and symptoms of heart failure; consider dosage reduction or discontinuation if heart failure occurs. (5.7)
- Hyperglycemia and Ketoacidosis Due to Insulin Pump Device Malfunction: Monitor glucose and administer HUMALOG U-100 by subcutaneous injection if pump malfunction occurs. (5.8)

6 ADVERSE REACTIONS

Adverse reactions associated with HUMALOG include hypoglycemia, allergic reactions, injection site reactions, lipodystrophy, pruritus, and rash. (6.1)

To report SUSPECTED ADVERSE REACTIONS, contact Eli Lilly and Company at 1-800-LillyRx (1-800-545-5979) or FDA at 1-800-FDA-1088 or www.fda.gov/medwatch.

7 DRUG INTERACTIONS

- Drugs that may increase the risk of hypoglycemia: antidiabetic agents, ACE inhibitors, angiotensin II receptor blocking agents, disopyramide, fibrates, fluoxetine, monoamine oxidase inhibitors, pentoxifylline, pramlintide, salicylates, somatostatin analog (e.g., octreotide), and sulfonamide antibiotics (7).
- Drugs that may decrease the blood glucose lowering effect: atypical antipsychotics, corticosteroids, danazol, diuretics, estrogens, glucagon, isoniazid, niacin, oral contraceptives, phenothiazines, progestogens (e.g., in oral contraceptives), protease inhibitors, somatropin, sympathomimetic agents (e.g., albuterol, epinephrine, terbutaline), and thyroid hormones (7).
- Drugs that may increase or decrease the blood glucose lowering effect: alcohol, beta-blockers, clonidine, lithium salts, and pentamidine (7).
- Drugs that may blunt the signs and symptoms of hypoglycemia: beta-blockers, clonidine, guanethidine, and reserpine (7).

FULL PRESCRIBING INFORMATION

1 INDICATIONS AND USAGE

HUMALOG is indicated to improve glycemic control in adult and pediatric patients with diabetes mellitus.

2 DOSAGE AND ADMINISTRATION

2.1 Important Administration Instructions

- Always check insulin labels before administration [see Warnings and Precautions (5.4)].
- Inspect HUMALOG visually before use. It should appear clear and colorless. Do not use HUMALOG if particulate matter or coloration is seen.
- Use HUMALOG prefilled pens with caution in patients with visual impairment that may rely on audible clicks to dial their dose.
- Do NOT mix HUMALOG U-100 with other insulins when using a continuous subcutaneous infusion pump.
- Do NOT transfer HUMALOG U-200 from the prefilled pen to a syringe for administration [see Warnings and Precautions (5.4)].
- Do NOT perform dose conversion when using any HUMALOG U-100 or U-200 prefilled pens. The dose window shows the number of insulin units to be delivered and no conversion is needed.

2.2 Administration Instructions for the Approved Routes of Administration

Subcutaneous Injection: HUMALOG U-100 or U-200

- Administer the dose of HUMALOG U-100 or HUMALOG U-200 within fifteen minutes before a meal or immediately after a meal by injection into the subcutaneous tissue of the abdominal wall, thigh, upper arm, or buttocks.
- Rotate the injection site within the same region from one injection to the next (abdominal wall, thigh, upper arm, or buttocks) to reduce the risk of lipodystrophy and localized cutaneous amyloidosis. Do not inject into areas of lipodystrophy or localized cutaneous amyloidosis [see Warnings and Precautions (5.2) and Adverse Reactions (6)].
- During changes to a patient's insulin regimen, increase the frequency of blood glucose monitoring [see Warnings and Precautions (5.2)].
- HUMALOG administered by subcutaneous injection should generally be used in regimens with an intermediate- or long-acting insulin.
- The HUMALOG U-100 KwikPen, HUMALOG U-100 Tempo Pen, HUMALOG U-200 KwikPen, and HUMALOG U-200 Tempo Pen each dial in 1 unit increments and delivers a maximum dose of 60 units per injection.
- The HUMALOG U-100 Junior KwikPen dials in 0.5 unit increments and delivers a maximum dose of 30 units per injection.

Subcutaneous Injection: Diluted HUMALOG U-100

- HUMALOG U-100 may be diluted with Sterile Diluent for HUMALOG for subcutaneous injection ONLY under medical supervision. Dilute one part HUMALOG U-100 to:
  - Nine parts diluent to yield a concentration one-tenth that of HUMALOG U-100 (equivalent to U-10).
  - One part diluent to yield a concentration one-half that of HUMALOG U-100 (equivalent to U-50).
- Diluted HUMALOG for subcutaneous injection may be stored for 28 days when refrigerated at 41°F (5°C) and for 14 days at room temperature up to 86°F (30°C).

Continuous Subcutaneous Infusion (Insulin Pump): HUMALOG U-100 ONLY

- Do NOT administer HUMALOG U-200 using a continuous subcutaneous infusion pump.
- Refer to the continuous subcutaneous insulin infusion pump user manual to see if HUMALOG can be used with the insulin pump. Use HUMALOG in accordance with the insulin pump system's instructions for use.
- Administer HUMALOG U-100 by continuous subcutaneous infusion in a region recommended in the instructions from the pump manufacturer. Rotate infusion sites within the same region to reduce the risk of lipodystrophy and localized cutaneous amyloidosis. Do not inject into areas of lipodystrophy or localized cutaneous amyloidosis [see Warnings and Precautions (5.2) and Adverse Reactions (6)].
- Train patients using continuous subcutaneous insulin infusion therapy to administer insulin by injection and have alternate insulin therapy available in case of insulin pump failure [see Warnings and Precautions (5.8)].
- During changes to a patient's insulin regimen, increase the frequency of blood glucose monitoring [see Warnings and Precautions (5.2)].
- Change HUMALOG U-100 in the pump reservoir at least every 7 days or according to the pump user manual, whichever is shorter.
- Change the infusion set and the infusion set insertion site according to the manufacturer's user manual.
- Do NOT dilute or mix HUMALOG U-100 when administering by continuous subcutaneous infusion.
- Do NOT expose HUMALOG U-100 in the pump reservoir to temperatures greater than 98.6°F (37°C).

Intravenous Administration: HUMALOG U-100 ONLY

- Do NOT administer HUMALOG U-200 intravenously.
- Administer HUMALOG U-100 intravenously ONLY under medical supervision with close monitoring of blood glucose and potassium levels to avoid hypoglycemia and hypokalemia [see Warnings and Precautions (5.3, 5.6)].
- Dilute HUMALOG U-100 to concentrations from 0.1 unit/mL to 1.0 unit/mL using 0.9% Sodium Chloride Injection, USP.
- Infusion bags prepared with HUMALOG U-100 are stable when stored in a refrigerator (2° to 8°C [36° to 46°F]) for 48 hours and then may be used at room temperature for up to an additional 48 hours.

2.3 Dosage Recommendations

- Individualize and adjust the dosage of HUMALOG based on route of administration, the individual's metabolic needs, blood glucose monitoring results and glycemic control goal.
- When switching from another insulin to HUMALOG, a different dosage of HUMALOG may be needed [see Warnings and Precautions (5.2)].
- Dosage modifications may be needed with changes in physical activity, changes in meal patterns (i.e., macronutrient content or timing of food intake), changes in renal or hepatic function or during acute illness [see Warnings and Precautions (5.2, 5.3) and Use in Specific Populations (8.6, 8.7)].
- Do NOT perform dose conversion when using any HUMALOG U-100 or U-200 prefilled pens. The dose window shows the number of insulin units to be delivered and no conversion is needed.

2.4 Dosage Modifications for Drug Interactions

Dosage modification may be needed when HUMALOG is used concomitantly with certain drugs [see Drug Interactions (7)].

2.5 Instructions for Mixing with Other Insulins

The table below includes administration instructions regarding mixing HUMALOG U-100 and HUMALOG U-200 with other insulins.

HUMALOG U-100 subcutaneous injection route | - HUMALOG U-100 may be mixed with NPH insulin preparations ONLY. - If HUMALOG U-100 is mixed with NPH insulin, HUMALOG U-100 should be drawn into the syringe first. Injection should occur immediately after mixing.
HUMALOG U-100 continuous subcutaneous infusion route (Insulin Pump) | Do NOT mix HUMALOG U-100 with any other insulin.
HUMALOG U-200 subcutaneous injection route | Do NOT mix with any other insulin.

3 DOSAGE FORMS AND STRENGTHS

Injection: 100 units/mL (U-100) clear and colorless solution available as:

- 10 mL multiple-dose vial
- 3 mL multiple-dose vial
- 3 mL single-patient-use KwikPen prefilled pen
- 3 mL single-patient-use Tempo Pen prefilled pen
- 3 mL single-patient-use Junior KwikPen prefilled pen
- 3 mL single-patient-use cartridges

Injection: 200 units/mL (U-200) clear and colorless solution available as:

- 3 mL single-patient-use KwikPen prefilled pen
- 3 mL single-patient-use Tempo Pen prefilled pen

4 CONTRAINDICATIONS

HUMALOG is contraindicated:

- during episodes of hypoglycemia [see Warnings and Precautions (5.3)].
- in patients who are hypersensitive to insulin lispro or to any of the excipients in HUMALOG [see Warnings and Precautions (5.5)].

5 WARNINGS AND PRECAUTIONS

5.1 Never Share a HUMALOG Prefilled Pen, Cartridge, Reusable Pen Compatible with Lilly 3 mL Cartridges^1, or Syringe Between Patients

HUMALOG prefilled pens, cartridges, and reusable pens compatible with Lilly 3 mL cartridges must never be shared between patients, even if the needle is changed. Patients using HUMALOG vials must never share needles or syringes with another person. Sharing poses a risk for transmission of blood-borne pathogens.

5.2 Hyperglycemia or Hypoglycemia with Changes in Insulin Regimen

Changes in an insulin regimen (e.g., insulin strength, manufacturer, type, injection site or method of administration) may affect glycemic control and predispose to hypoglycemia [see Warnings and Precautions (5.3)] or hyperglycemia. Repeated insulin injections into areas of lipodystrophy or localized cutaneous amyloidosis have been reported to result in hyperglycemia; and a sudden change in the injection site (to an unaffected area) has been reported to result in hypoglycemia [see Adverse Reactions (6)].

Make any changes to a patient's insulin regimen under close medical supervision with increased frequency of blood glucose monitoring. Advise patients who have repeatedly injected into areas of lipodystrophy or localized cutaneous amyloidosis to change the injection site to unaffected areas and closely monitor for hypoglycemia. For patients with type 2 diabetes, dosage adjustments of concomitant antidiabetic products may be needed.

5.3 Hypoglycemia

Hypoglycemia is the most common adverse reaction associated with insulins, including HUMALOG. Severe hypoglycemia can cause seizures, may be life-threatening, or cause death. Hypoglycemia can impair concentration ability and reaction time; this may place an individual and others at risk in situations where these abilities are important (e.g., driving or operating other machinery).

Hypoglycemia can happen suddenly, and symptoms may differ in each individual and change over time in the same individual. Symptomatic awareness of hypoglycemia may be less pronounced in patients with longstanding diabetes, in patients with diabetic nerve disease, in patients using medications that block the sympathetic nervous system (e.g., beta-blockers) [see Drug Interactions (7)], or in patients who experience recurrent hypoglycemia.

Risk Factors for Hypoglycemia

The risk of hypoglycemia after an injection is related to the duration of action of the insulin and, in general, is highest when the glucose lowering effect of the insulin is maximal. As with all insulins, the glucose lowering effect time course of HUMALOG may vary in different individuals or at different times in the same individual and depends on many conditions, including the area of injection as well as the injection site blood supply and temperature [see Clinical Pharmacology (12.2)]. Other factors which may increase the risk of hypoglycemia include changes in meal pattern (e.g., macronutrient content or timing of meals), changes in level of physical activity, or changes to co-administered medication [see Drug Interactions (7)]. Patients with renal or hepatic impairment may be at higher risk of hypoglycemia [see Use in Specific Populations (8.6, 8.7)].

Risk Mitigation Strategies for Hypoglycemia

Patients and caregivers must be educated to recognize and manage hypoglycemia. Self-monitoring of blood glucose plays an essential role in the prevention and management of hypoglycemia. In patients at higher risk for hypoglycemia and patients who have reduced symptomatic awareness of hypoglycemia, increased frequency of blood glucose monitoring is recommended.

5.4 Hypoglycemia Due to Medication Errors

Accidental mix-ups between insulin products have been reported. To avoid medication errors between HUMALOG and other insulins, instruct patients to always check the insulin label before each injection.

Do not transfer HUMALOG U-200 from the HUMALOG prefilled pens to a syringe. The markings on the insulin syringe will not measure the dose correctly and can result in overdosage and severe hypoglycemia [see Dosage and Administration (2.1) and Warnings and Precautions (5.3)].

5.5 Hypersensitivity Reactions

Severe, life-threatening, generalized allergy, including anaphylaxis, can occur with insulins, including HUMALOG. If hypersensitivity reactions occur, discontinue HUMALOG; treat per standard of care and monitor until symptoms and signs resolve [see Adverse Reactions (6.1)]. HUMALOG is contraindicated in patients who have had hypersensitivity reactions to insulin lispro or any of the excipients in HUMALOG [see Contraindications (4)].

5.6 Hypokalemia

All insulins, including HUMALOG, cause a shift in potassium from the extracellular to intracellular space, possibly leading to hypokalemia. Untreated hypokalemia may cause respiratory paralysis, ventricular arrhythmia, and death. Monitor potassium levels in patients at risk for hypokalemia if indicated (e.g., patients using potassium-lowering medications, patients taking medications sensitive to serum potassium concentrations).

5.7 Fluid Retention and Heart Failure with Concomitant Use of PPAR-gamma Agonists

Thiazolidinediones (TZDs), which are peroxisome proliferator-activated receptor (PPAR)-gamma agonists, can cause dose-related fluid retention, particularly when used in combination with insulin. Fluid retention may lead to or exacerbate heart failure. Patients treated with insulin, including HUMALOG, and a PPAR-gamma agonist should be observed for signs and symptoms of heart failure. If heart failure develops, it should be managed according to current standards of care, and discontinuation or dose reduction of the PPAR-gamma agonist must be considered.

5.8 Hyperglycemia and Ketoacidosis Due to Insulin Pump Device Malfunction

Malfunction of the insulin pump or insulin infusion set or insulin degradation can rapidly lead to hyperglycemia and ketoacidosis. Prompt identification and correction of the cause of hyperglycemia or ketosis is necessary. Interim subcutaneous injections with HUMALOG may be required. Patients using continuous subcutaneous insulin infusion pump therapy must be trained to administer insulin by injection and have alternate insulin therapy available in case of pump failure [see How Supplied/Storage and Handling (16.2) and Patient Counseling Information (17)].

6 ADVERSE REACTIONS

The following adverse reactions are discussed elsewhere:

- Hypoglycemia [see Warnings and Precautions (5.3)].
- Hypoglycemia Due to Medication Errors [see Warnings and Precautions (5.4)].
- Hypersensitivity Reactions [see Warnings and Precautions (5.5)].
- Hypokalemia [see Warnings and Precautions (5.6)].

6.1 Clinical Trials Experience

Because clinical trials are conducted under widely varying designs, the adverse reaction rates reported in one clinical trial may not be easily compared with those rates reported in another clinical trial, and may not reflect the rates actually observed in clinical practice.

Common adverse reactions, excluding hypoglycemia, were defined as events that occurred in ≥5% of patients treated with insulin lispro or regular human insulin. The frequencies of adverse reactions during HUMALOG clinical trials in patients with type 1 diabetes mellitus and type 2 diabetes mellitus are listed in the tables below.

Table 1: Adverse Reactions That Occurred in ≥5% in Patients with Type 1 Diabetes Mellitus
 | HUMALOG (%) (n=81) | Regular human insulin (%) (n=86)
Flu syndrome | 34.6 | 32.6
Pharyngitis | 33.3 | 33.7
Rhinitis | 24.7 | 29.1
Headache | 29.6 | 22.1
Pain | 19.8 | 16.3
Cough increased | 17.3 | 17.4
Infection | 13.6 | 20.9
Nausea | 6.2 | 15.1
Accidental injury | 8.6 | 11.6
Surgical procedure | 6.2 | 14.0
Fever | 6.2 | 11.6
Abdominal pain | 7.4 | 8.1
Asthenia | 7.4 | 8.1
Bronchitis | 7.4 | 7.0
Diarrhea | 8.6 | 5.8
Dysmenorrhea | 6.2 | 7.0
Myalgia | 7.4 | 5.8
Urinary tract infection | 6.2 | 4.7

Table 2: Adverse Reactions That Occurred in ≥5% in Patients with Type 2 Diabetes Mellitus
 | HUMALOG (%) (n=714) | Regular human insulin (%) (n=709)
Headache | 11.6 | 9.3
Pain | 10.8 | 10.0
Infection | 10.1 | 7.6
Pharyngitis | 6.6 | 8.2
Rhinitis | 8.1 | 6.6
Flu syndrome | 6.2 | 8.2
Surgical procedure | 7.4 | 6.8

Insulin initiation and intensification of glucose control

Intensification or rapid improvement in glucose control has been associated with a transitory, reversible ophthalmologic refraction disorder, worsening of diabetic retinopathy, and acute painful peripheral neuropathy. However, long-term glycemic control decreases the risk of diabetic retinopathy and neuropathy.

Hypoglycemia

Hypoglycemia is the most commonly observed adverse reaction in patients using insulin, including HUMALOG.

Lipodystrophy

Long-term use of insulin, including HUMALOG, can cause lipodystrophy at the site of repeated insulin injections or infusion. Lipodystrophy includes lipohypertrophy (thickening of adipose tissue) and lipoatrophy (thinning of adipose tissue), and may affect insulin absorption [see Dosage and Administration (2.2)].

Weight gain

Weight gain can occur with insulins, including HUMALOG, and has been attributed to the anabolic effects of insulin and the decrease in glucosuria.

Peripheral Edema

Insulins, including HUMALOG, may cause sodium retention and edema, particularly if previously poor metabolic control is improved by intensified insulin therapy.

Adverse Reactions with Continuous Subcutaneous Insulin Infusion (CSII) — HUMALOG U-100

In a 12-week, randomized, crossover study in adult patients with type 1 diabetes (n=39), the rates of catheter occlusions and infusion site reactions were similar for HUMALOG U-100 and regular human insulin treated patients (see Table 3).

Table 3: Catheter Occlusions and Infusion Site Reactions
 | HUMALOG U-100 (n=38) | Regular human insulin (n=39)
Catheter occlusions/month | 0.09 | 0.10
Infusion site reactions | 2.6% (1/38) | 2.6% (1/39)

In a randomized, 16-week, open-label, parallel design study of pediatric patients with type 1 diabetes, adverse reactions related to infusion-site reactions were similar for insulin lispro and insulin aspart (21% of 100 patients versus 17% of 198 patients, respectively). In both groups, the most frequently reported infusion site reactions were infusion site erythema and infusion site reaction.

Allergic Reactions

Local Allergy — As with any insulin, patients taking HUMALOG may experience redness, swelling, or itching at the site of the injection. These minor reactions usually resolve in a few days to a few weeks, but in some occasions, may require discontinuation of HUMALOG.

Systemic Allergy — Severe, life-threatening, generalized allergy, including anaphylaxis, may occur with any insulin, including HUMALOG. Generalized allergy to insulin may cause whole body rash (including pruritus), dyspnea, wheezing, hypotension, tachycardia, or diaphoresis.

In controlled clinical trials, pruritus (with or without rash) was seen in 17 patients receiving regular human insulin (n=2969) and 30 patients receiving HUMALOG (n=2944).

Localized reactions and generalized myalgias have been reported with injected metacresol, which is an excipient in HUMALOG [see Contraindications (4)].

Antibody Production

In large clinical trials with patients with type 1 (n=509) and type 2 (n=262) diabetes mellitus, anti-insulin antibody (insulin lispro-specific antibodies, insulin-specific antibodies, cross-reactive antibodies) formation was evaluated in patients receiving both regular human insulin and HUMALOG (including patients previously treated with human insulin and naive patients). As expected, the largest increase in the antibody levels occurred in patients new to insulin therapy. The antibody levels peaked by 12 months and declined over the remaining years of the study. These antibodies do not appear to cause deterioration in glycemic control or necessitate an increase in insulin dose. There was no statistically significant relationship between the change in the total daily insulin dose and the change in percent antibody binding for any of the antibody types.

6.2 Postmarketing Experience

The following additional adverse reactions have been identified during post-approval use of HUMALOG. Because these reactions are reported voluntarily from a population of uncertain size, it is not always possible to reliably estimate their frequency or establish a causal relationship to drug exposure.

Medication errors in which other insulins have been accidentally substituted for HUMALOG have been identified during post-approval use.

Localized cutaneous amyloidosis at the injection site has occurred. Hyperglycemia has been reported with repeated insulin injections into areas of localized cutaneous amyloidosis; hypoglycemia has been reported with a sudden change to an unaffected injection site.

7 DRUG INTERACTIONS

The table below includes clinically significant drug interactions with HUMALOG.

Drugs That May Increase the Risk of Hypoglycemia
Drugs: | Antidiabetic agents, ACE inhibitors, angiotensin II receptor blocking agents, disopyramide, fibrates, fluoxetine, monoamine oxidase inhibitors, pentoxifylline, pramlintide, salicylates, somatostatin analogs (e.g., octreotide), and sulfonamide antibiotics.
Intervention: | Dose adjustment and increased frequency of glucose monitoring may be required when HUMALOG is co-administered with these drugs.
Drugs That May Decrease the Blood Glucose Lowering Effect of HUMALOG
Drugs: | Atypical antipsychotics (e.g., olanzapine and clozapine), corticosteroids, danazol, diuretics, estrogens, glucagon, isoniazid, niacin, oral contraceptives, phenothiazines, progestogens (e.g., in oral contraceptives), protease inhibitors, somatropin, sympathomimetic agents (e.g., albuterol, epinephrine, terbutaline), and thyroid hormones.
Intervention: | Dose adjustment and increased frequency of glucose monitoring may be required when HUMALOG is co-administered with these drugs.
Drugs That May Increase or Decrease the Blood Glucose Lowering Effect of HUMALOG
Drugs: | Alcohol, beta-blockers, clonidine, and lithium salts. Pentamidine may cause hypoglycemia, which may sometimes be followed by hyperglycemia.
Intervention: | Dose adjustment and increased frequency of glucose monitoring may be required when HUMALOG is co-administered with these drugs.
Drugs That May Blunt Signs and Symptoms of Hypoglycemia
Drugs: | Beta-blockers, clonidine, guanethidine and reserpine.
Intervention: | Increased frequency of glucose monitoring may be required when HUMALOG is co-administered with these drugs.

8 USE IN SPECIFIC POPULATIONS

8.1 Pregnancy

Risk Summary

Published studies with insulin lispro used during pregnancy have not reported an association between insulin lispro and the induction of major birth defects, miscarriage, or adverse maternal or fetal outcomes (see Data). There are risks to the mother and fetus associated with poorly controlled diabetes in pregnancy (see Clinical Considerations).

Pregnant rats and rabbits were exposed to insulin lispro in animal reproduction studies during organogenesis. No adverse effects on embryo/fetal viability or morphology were observed in offspring of rats exposed to insulin lispro at a dose approximately 3 times the human subcutaneous dose of 1 unit insulin lispro/kg/day. No adverse effects on embryo/fetal development were observed in offspring of rabbits exposed to insulin lispro at doses up to approximately 0.2 times the human subcutaneous dose of 1 unit/kg/day (see Data).

The estimated background risk of major birth defects is 6-10% in women with pre-gestational diabetes with a HbA1c >7 and has been reported to be as high as 20-25% in women with a HbA1c >10. The estimated background risk of miscarriage for the indicated population is unknown. In the U.S. general population, the estimated background risk of major birth defects and miscarriage in clinically recognized pregnancies is 2-4% and 15-20%, respectively.

Clinical Considerations

Disease-associated maternal and/or embryo/fetal risk

Poorly controlled diabetes in pregnancy increases the maternal risk for diabetic ketoacidosis, pre-eclampsia, spontaneous abortions, preterm delivery, and delivery complications. Poorly controlled diabetes increases the fetal risk for major birth defects, stillbirth, and macrosomia related morbidity.

Data

Human Data

Published data from retrospective studies and meta-analyses do not report an association with insulin lispro and major birth defects, miscarriage, or adverse maternal or fetal outcomes when insulin lispro is used during pregnancy. However, these studies cannot definitely establish or exclude the absence of any risk because of methodological limitations including small sample size, selection bias, confounding by unmeasured factors, and some lacking comparator groups.

Animal Data

In a combined fertility and embryo-fetal development study, female rats were given subcutaneous insulin lispro injections of 1, 5, and 20 units/kg/day (0.2, 0.8, and 3 times the human subcutaneous dose of 1 unit insulin lispro/kg/day, based on units/body surface area, respectively) from 2 weeks prior to cohabitation through Gestation Day 19. There were no adverse effects on female fertility, implantation, or fetal viability and morphology. However, fetal growth retardation was produced at the 20 units/kg/day-dose as indicated by decreased fetal weight and an increased incidence of fetal runts/litter.

In an embryo-fetal development study in pregnant rabbits, insulin lispro doses of 0.1, 0.25, and 0.75 unit/kg/day (0.03, 0.08, and 0.2 times the human subcutaneous dose of 1 unit insulin lispro/kg/day, based on units/body surface area, respectively) were injected subcutaneously on Gestation days 7 through 19. There were no adverse effects on fetal viability, weight, and morphology at any dose.

8.2 Lactation

Risk Summary

Available data from published literature suggests that exogenous human insulin products, including insulin lispro, are transferred into human milk. There are no adverse reactions reported in breastfed infants in the literature. There are no data on the effects of exogenous human insulin products, including insulin lispro, on milk production. The developmental and health benefits of breastfeeding should be considered along with the mother's clinical need for insulin, any potential adverse effects on the breastfed child from HUMALOG or from the underlying maternal condition.

8.4 Pediatric Use

The safety and effectiveness of HUMALOG to improve glycemic control have been established in pediatric patients with diabetes mellitus. Use of HUMALOG for this indication is supported by evidence from adequate and well-controlled studies in 831 pediatric patients with type 1 diabetes mellitus aged 3 years and older and from studies in adults with diabetes mellitus [see Adverse Reactions (6.1), Clinical Pharmacology (12.3), and Clinical Studies (14)].

8.5 Geriatric Use

Of the total number of patients (n=2,834) in eight clinical studies of HUMALOG, twelve percent (n=338) were 65 years of age or over. The majority of these patients had type 2 diabetes. HbA1c values and hypoglycemia rates did not differ by age. Pharmacokinetic/pharmacodynamic studies to assess the effect of age on the onset of HUMALOG action have not been performed.

8.6 Renal Impairment

Patients with renal impairment may be at increased risk of hypoglycemia and may require more frequent HUMALOG dose adjustment and more frequent blood glucose monitoring [see Clinical Pharmacology (12.3)].

8.7 Hepatic Impairment

Patients with hepatic impairment may be at increased risk of hypoglycemia and may require more frequent HUMALOG dose adjustment and more frequent blood glucose monitoring [see Clinical Pharmacology (12.3)].

10 OVERDOSAGE

Excess insulin administration may cause hypoglycemia and hypokalemia. Mild episodes of hypoglycemia usually can be treated with oral glucose. Adjustments in drug dosage, meal patterns, or exercise may be needed. More severe episodes with coma, seizure, or neurologic impairment may be treated with a glucagon product for emergency use or concentrated intravenous glucose. Sustained carbohydrate intake and observation may be necessary because hypoglycemia may recur after apparent clinical recovery. Hypokalemia must be corrected appropriately.

11 DESCRIPTION

Insulin lispro is a rapid-acting human insulin analog produced by recombinant DNA technology utilizing a non-pathogenic laboratory strain of Escherichia coli. Insulin lispro differs from human insulin in that the amino acid proline at position B28 is replaced by lysine and the lysine in position B29 is replaced by proline. Chemically, it is Lys(B28), Pro(B29) human insulin analog and has the empirical formula C257H383N65O77S6 and a molecular weight of 5.808 kDa, both identical to that of human insulin.

Insulin lispro has the following primary structure:

HUMALOG (insulin lispro) injection is a sterile, clear, and colorless solution for subcutaneous or intravenous use.

Each mL of HUMALOG U-100 contains 100 units of insulin lispro, and the inactive ingredients: dibasic sodium phosphate (1.0 mg), glycerin (16 mg), metacresol (3.15 mg), trace amounts of phenol, zinc oxide (content adjusted to provide 0.0197 mg zinc ion), and Water for Injection, USP.

Each mL of HUMALOG U-200 contains 200 units of insulin lispro, and the inactive ingredients: glycerin (16 mg), metacresol (3.15 mg), trace amounts of phenol, tromethamine (5 mg), zinc oxide (content adjusted to provide 0.046 mg zinc ion), and Water for Injection, USP.

HUMALOG has a pH of 7.0 to 7.8.

Hydrochloric acid 10% and/or sodium hydroxide 10% is added to adjust the pH.

12 CLINICAL PHARMACOLOGY

12.1 Mechanism of Action

Regulation of glucose metabolism is the primary activity of insulins and insulin analogs, including insulin lispro. Insulins lower blood glucose by stimulating peripheral glucose uptake by skeletal muscle and fat, and by inhibiting hepatic glucose production. Insulins inhibit lipolysis and proteolysis, and enhance protein synthesis.

12.2 Pharmacodynamics

HUMALOG has been shown to be equipotent to human insulin on a molar basis. One unit of HUMALOG has the same glucose-lowering effect as one unit of regular human insulin. Studies in normal volunteers and patients with diabetes demonstrated that HUMALOG has a more rapid onset of action and a shorter duration of activity than regular human insulin when given subcutaneously.

The time course of action of insulin and insulin analogs, such as HUMALOG, may vary considerably in different individuals or within the same individual. The parameters of HUMALOG activity (time of onset, peak time, and duration) as designated in Figure 1 should be considered only as general guidelines. The rate of insulin absorption, and consequently the onset of activity are known to be affected by the site of injection, exercise, and other variables [see Warnings and Precautions (5.2)].

Figure 1: Blood Glucose Levels After Subcutaneous Injection of Regular Human Insulin or HUMALOG (0.2 unit/kg) Immediately Before a High Carbohydrate Meal in 10 Patients with Type 1 Diabetesa.

a Baseline insulin concentration was maintained by infusion of 0.2 mU/min/kg human insulin.

Intravenous Administration of HUMALOG U-100 — The glucose lowering effect of intravenously administered HUMALOG was tested in 21 patients with type 1 diabetes. For the study, the patients' usual doses of insulin were held and blood glucose concentrations were allowed to reach a stable range of 200 to 260 mg/dL during a one to three hours run-in phase. The run-in phase was followed by a 6-hour assessment phase. During the assessment phase, patients received intravenous HUMALOG at an initial infusion rate of 0.5 units/hour. The infusion rate of HUMALOG could be adjusted at regular timed intervals to achieve and maintain blood glucose concentrations between 100 to 160 mg/dL.

The mean blood glucose levels during the assessment phase for patients on HUMALOG therapy are summarized below in Table 4. All patients achieved the targeted glucose range at some point during the 6-hour assessment phase. At the endpoint, blood glucose was within the target range (100 to 160 mg/dL) for 17 of 20 patients treated with HUMALOG. The average time (±SE) required to attain near normoglycemia was 129 ± 14 minutes for HUMALOG.

Table 4: Mean Blood Glucose Concentrations (mg/dL) During Intravenous Infusions of HUMALOG U-100
Time from Start of Infusion (minutes) | Mean Blood Glucose (mg/dL) Intravenousa
0 | 224 ± 16
30 | 205 ± 21
60 | 195 ± 20
120 | 165 ± 26
180 | 140 ± 26
240 | 123 ± 20
300 | 120 ± 27
360 | 122 ± 25
a Results shown as mean ± SD

The pharmacodynamics of a single 20 unit dose of HUMALOG U-200 administered subcutaneously were compared to the pharmacodynamics of a single 20 unit dose of HUMALOG U-100 administered subcutaneously in a euglycemic clamp study enrolling healthy subjects. In this study, the overall, maximum, and time to maximum glucose lowering effect were similar between HUMALOG U-200 and HUMALOG U-100. The mean area under the glucose infusion rate curves (measure of overall pharmacodynamic effect) were 125 g and 126 g for HUMALOG U-200 and HUMALOG U-100, respectively. The maximum glucose infusion rate was 534 mg/min and 559 mg/min and the corresponding median time (min, max) to maximum effect were 2.8 h (0.5 h – 6.3 h) and 2.4 h (0.5 h – 4.7 h) for HUMALOG U-200 and HUMALOG U-100, respectively.

12.3 Pharmacokinetics

Absorption and Bioavailability — Studies in healthy volunteers and patients with diabetes demonstrated that HUMALOG is absorbed more quickly than regular human insulin. In healthy volunteers given subcutaneous doses of HUMALOG ranging from 0.1 to 0.4 unit/kg, peak serum levels were seen 30 to 90 minutes after dosing. When healthy volunteers received equivalent doses of regular human insulin, peak insulin levels occurred between 50 to 120 minutes after dosing. Similar results were seen in patients with type 1 diabetes (see Figure 2).

Figure 2: Serum HUMALOG and Insulin Levels After Subcutaneous Injection of Regular Human Insulin or HUMALOG (0.2 unit/kg) Immediately Before a High Carbohydrate Meal in 10 Patients with Type 1 Diabetesa.

a Baseline insulin concentration was maintained by infusion of 0.2 mU/min/kg human insulin.

HUMALOG U-100 was absorbed at a consistently faster rate than regular human insulin in healthy male volunteers given 0.2 unit/kg at abdominal, deltoid, or femoral subcutaneous sites. After HUMALOG was administered in the abdomen, serum drug levels were higher and the duration of action was slightly shorter than after deltoid or thigh administration. Bioavailability of HUMALOG is similar to that of regular human insulin. The absolute bioavailability after subcutaneous injection ranges from 55% to 77% with doses between 0.1 to 0.2 unit/kg, inclusive.

The results of a study in healthy subjects demonstrated that HUMALOG U-200 is bioequivalent to HUMALOG U-100 following administration of a single 20 unit dose.

The mean observed area under the serum insulin concentration-time curve from time zero to infinity was 2360 pmol hr/L and 2390 pmol hr/L for HUMALOG U-200 and HUMALOG U-100, respectively. The corresponding mean peak serum insulin concentration was 795 pmol/L and 909 pmol/L for HUMALOG U-200 and HUMALOG U-100, respectively. The median time to maximum concentration was 1.0 hour for both formulations.

Distribution — When administered intravenously as bolus injections of 0.1 and 0.2 U/kg dose in two separate groups of healthy subjects, the mean volume of distribution of HUMALOG appeared to decrease with increase in dose (1.55 and 0.72 L/kg, respectively) in contrast to that of regular human insulin for which, the volume of distribution was comparable across the two dose groups (1.37 and 1.12 L/kg for 0.1 and 0.2 U/kg dose, respectively).

Metabolism — Human metabolism studies have not been conducted. However, animal studies indicate that the metabolism of HUMALOG is identical to that of regular human insulin.

Elimination — After subcutaneous administration of HUMALOG, the t1/2 is shorter than that of regular human insulin (1 versus 1.5 hours, respectively). When administered intravenously, HUMALOG and regular human insulin demonstrated similar dose-dependent clearance, with a mean clearance of 21.0 mL/min/kg and 21.4 mL/min/kg, respectively (0.1 unit/kg dose), and 9.6 mL/min/kg and 9.4 mL/min/kg, respectively (0.2 unit/kg dose). Accordingly, HUMALOG demonstrated a mean t1/2 of 0.85 hours (51 minutes) and 0.92 hours (55 minutes), respectively for 0.1 unit/kg and 0.2 unit/kg doses, and regular human insulin mean t1/2 was 0.79 hours (47 minutes) and 1.28 hours (77 minutes), respectively for 0.1 unit/kg and 0.2 unit/kg doses.

Specific Populations

The effects of age, gender, race, obesity, pregnancy, or smoking on the pharmacokinetics of HUMALOG have not been studied.

Renal Impairment — Type 2 diabetic patients with varying degree of renal impairment showed no difference in pharmacokinetics of regular insulin and HUMALOG. However, the sensitivity of the patients to insulin did change, with an increased response to insulin as the renal function declined. Some studies with human insulin have shown increased circulating levels of insulin in patients with renal impairment [see Use in Specific Populations (8.6)].

Hepatic Impairment — Type 2 diabetic patients with impaired hepatic function showed no effect on the pharmacokinetics of HUMALOG as compared to patients with no hepatic dysfunction. However, some studies with human insulin have shown increased circulating levels of insulin in patients with liver failure [see Use in Specific Populations (8.7)].

13 NONCLINICAL TOXICOLOGY

13.1 Carcinogenesis, Mutagenesis, Impairment of Fertility

Standard 2-year carcinogenicity studies in animals have not been performed. In Fischer 344 rats, a 12-month repeat-dose toxicity study was conducted with insulin lispro at subcutaneous doses of 20 and 200 units/kg/day (approximately 3 and 32 times the human subcutaneous dose of 1 unit/kg/day, based on units/body surface area). Insulin lispro did not produce important target organ toxicity including mammary tumors at any dose.

Insulin lispro was not mutagenic in the following genetic toxicity assays: bacterial mutation, unscheduled DNA synthesis, mouse lymphoma, chromosomal aberration and micronucleus assays.

Male fertility was not compromised when male rats given subcutaneous insulin lispro injections of 5 and 20 units/kg/day (0.8 and 3 times the human subcutaneous dose of 1 unit/kg/day, based on units/body surface area) for 6 months were mated with untreated female rats. In a combined fertility, perinatal, and postnatal study in male and female rats given 1, 5, and 20 units/kg/day subcutaneously (0.2, 0.8, and 3 times the human subcutaneous dose of 1 unit/kg/day, based on units/body surface area), mating and fertility were not adversely affected in either gender at any dose.

13.2 Animal Toxicology and/or Pharmacology

In standard biological assays in fasted rabbits, 0.2 unit/kg of insulin lispro injected subcutaneously had the same glucose-lowering effect and had a more rapid onset of action as 0.2 unit/kg of regular human insulin.

14 CLINICAL STUDIES

The safety and efficacy of HUMALOG U-100 were studied in pediatric and adult patients with type 1 diabetes (n=789) and adult patients with type 2 diabetes (n=722).

14.1 Type 1 Diabetes – Adults and Pediatric Patients Aged 12 Years and Older

A 12-month, randomized, parallel, open-label, active-controlled study was conducted in patients with type 1 diabetes to assess the safety and efficacy of HUMALOG (n=81) compared with Humulin® R [insulin human injection (100 units/mL)] (n=86). HUMALOG was administered by subcutaneous injection immediately prior to meals and Humulin R was administered 30 to 45 minutes before meals. Humulin® U [ULTRALENTE® human insulin (rDNA origin) extended zinc suspension] was administered once or twice daily as the basal insulin. There was a 2- to 4-week run-in period with Humulin R and Humulin U before randomization. Most patients were Caucasian (97%). Forty-seven percent of the patients were male. The mean age was 31 years (range 12 to 70 years). Glycemic control, the total daily doses of HUMALOG and Humulin R, and the incidence of severe hypoglycemia (as determined by the number of events that were not self-treated) were similar in the two treatment groups. There were no episodes of diabetic ketoacidosis in either treatment group.

Table 5: Type 1 Diabetes Mellitus – Adults and Pediatric Patients Aged 12 years and Older
Treatment Duration Treatment in Combination with: | 12 months Humulin U
 | HUMALOG | Humulin R
N | 81 | 86
Baseline HbA1c (%)a | 8.2 ± 1.4 | 8.3 ± 1.7
Change from baseline HbA1c (%)a | -0.1 ± 0.9 | 0.1 ± 1.1
Treatment Difference in HbA1c Mean (95% confidence interval) | 0.4 (0.0, 0.8)
Baseline short-acting insulin dose (units/kg/day) | 0.3 ± 0.1 | 0.3 ± 0.1
End-of-Study short-acting insulin dose (units/kg/day) | 0.3 ± 0.1 | 0.3 ± 0.1
Change from baseline short-acting insulin dose (units/kg/day) | 0.0 ± 0.1 | 0.0 ± 0.1
Baseline Body weight (kg) | 72 ± 12.7 | 71 ± 11.3
Weight change from baseline (kg) | 1.4 ± 3.6 | 1.0 ± 2.6
Patients with severe hypoglycemia (n, %)b | 14 (17%) | 18 (21%)
a Values are Mean ± SD
b Severe hypoglycemia refers to hypoglycemia for which patients were not able to self-treat.

14.2 Type 1 Diabetes – Pediatric Patients

An 8-month, crossover study of pediatric patients with type 1 diabetes (n=463), aged 9 to 19 years, compared two subcutaneous multiple-dose treatment regimens: HUMALOG or Humulin R, both administered with Humulin N (NPH human insulin) as the basal insulin. HUMALOG achieved glycemic control comparable to Humulin R, as measured by HbA1c (see Table 6), and both treatment groups had a comparable incidence of hypoglycemia. In a 9-month, crossover study of pediatric patients (n=60) with type 1 diabetes, aged 3 to 11 years, HUMALOG administered immediately before meals, HUMALOG administered immediately after meals and Humulin R administered 30 minutes before meals resulted in similar glycemic control, as measured by HbA1c, and incidence of hypoglycemia, regardless of treatment group.

Table 6: Pediatric Subcutaneous Administration of HUMALOG in Type 1 Diabetes
 |  | End point
 | Baseline | HUMALOG + NPH | Humulin R + NPH
HbA1c (%)a | 8.6 ± 1.5 | 8.7 ± 1.5 | 8.7 ± 1.6
Change from baseline HbA1c (%)a | — | 0.1 ± 1.1 | 0.1 ± 1.3
Short-acting insulin dose (units/kg/day)a | 0.5 ± 0.2 | 0.5 ± 0.2 | 0.5 ± 0.2
Change from baseline short-acting insulin dose (units/kg/day)a | — | 0.01 ± 0.1 | -0.01 ± 0.1
Body weight (kg)a | 59.1 ± 13.1 | 61.1 ± 12.7 | 61.4 ± 12.9
Weight change from baseline (kg)a | — | 2.0 ± 3.1 | 2.3 ± 3.0
Patients with severe hypoglycemia (n, %)b | — | 5 (1.1%) | 5 (1.1%)
Diabetic ketoacidosis (n, %) | — | 11 (2.4%) | 9 (1.9%)
a Values are Mean ± SD
b Severe hypoglycemia refers to hypoglycemia that required glucagon or glucose injection or resulted in coma.

14.3 Type 1 Diabetes – Adults Continuous Subcutaneous Insulin Infusion

To evaluate the administration of HUMALOG U-100 via external insulin pumps, two open-label, crossover design studies were performed in patients with type 1 diabetes. One study involved 39 patients, ages 19 to 58 years, treated for 24 weeks with HUMALOG or regular human insulin. After 12 weeks of treatment, the mean HbA1c values decreased from 7.8% to 7.2% in the HUMALOG-treated patients and from 7.8% to 7.5% in the regular human insulin-treated patients. Another study involved 60 patients (mean age 39, range 15 to 58 years) treated for 24 weeks with either HUMALOG or buffered regular human insulin. After 12 weeks of treatment, the mean HbA1c values decreased from 7.7% to 7.4% in the HUMALOG-treated patients and remained unchanged from 7.7% in the buffered regular human insulin-treated patients. Rates of hypoglycemia were comparable between treatment groups in both studies.

14.4 Type 1 Diabetes – Pediatric Patients: Continuous Subcutaneous Insulin Infusion

A randomized, 16-week, open-label, parallel design, study of pediatric patients with type 1 diabetes (n=298) aged 4 to 18 years compared two subcutaneous infusion regimens administered via an external insulin pump: insulin aspart (n=198) or HUMALOG U-100 (n=100). These two treatments resulted in comparable changes from baseline in HbA1c and comparable rates of hypoglycemia after 16 weeks of treatment (see Table 7). Infusion site reactions were similar between groups.

Table 7: Pediatric Insulin Pump Study in Type 1 Diabetes (16 weeks; n=298)
 | HUMALOG | Aspart
N | 100 | 198
Baseline HbA1c (%)a | 8.2 ± 0.8 | 8.0 ± 0.9
Change from Baseline HbA1c (%) | -0.1 ± 0.7 | -0.1 ± 0.8
Treatment Difference in HbA1c, Mean (95% confidence interval) | 0.1 (-0.3, 0.1)
Baseline insulin dose (units/kg/24 hours)a | 0.9 ± 0.3 | 0.9 ± 0.3
End-of-Study insulin dose (units/kg/24 hours)a | 0.9 ± 0.2 | 0.9 ± 0.2
Patients with severe hypoglycemia (n, %)b | 8 (8%) | 19 (10%)
Diabetic ketoacidosis (n, %) | 0 (0) | 1 (0.5%)
Baseline body weight (kg)a | 55.5 ± 19.0 | 54.1 ± 19.7
Weight Change from baseline (kg)a | 1.6 ± 2.1 | 1.8 ± 2.1
a Values are Mean ± SD
b Severe hypoglycemia refers to hypoglycemia associated with central nervous system symptoms and requiring the intervention of another person or hospitalization.

14.5 Type 2 Diabetes – Adults

A 6-month randomized, crossover, open-label, active-controlled study was conducted in insulin-treated patients with type 2 diabetes (n=722) to assess the safety and efficacy of HUMALOG for 3 months followed by Humulin R for 3 months or the reverse sequence. HUMALOG was administered by subcutaneous injection immediately before meals and Humulin R was administered 30 to 45 minutes before meals. Humulin® N [NPH human insulin (rDNA origin) isophane suspension] or Humulin U was administered once or twice daily as the basal insulin. All patients participated in a 2- to 4-week run-in period with Humulin R and Humulin N or Humulin U. Most of the patients were Caucasian (88%), and the numbers of men and women in each group were approximately equal. The mean age was 58.6 years (range 23.8 to 85 years). The average body mass index (BMI) was 28.2 kg/m^2. During the study, the majority of patients used Humulin N (84%) compared with Humulin U (16%) as their basal insulin. The reductions from baseline in HbA1c and the incidence of severe hypoglycemia (as determined by the number of events that were not self-treated) were similar between the two treatments from the combined groups (see Table 8).

Table 8: Type 2 Diabetes Mellitus — Adults
 |  | End point
 | Baseline | HUMALOG + Basal | Humulin R + Basal
HbA1c (%)a | 8.9 ± 1.7 | 8.2 ± 1.3 | 8.2 ± 1.4
Change from baseline HbA1c (%)a | — | -0.7 ± 1.4 | -0.7 ± 1.3
Short-acting insulin dose (units/kg/day)a | 0.3 ± 0.2 | 0.3 ± 0.2 | 0.3 ± 0.2
Change from baseline short-acting insulin dose (units/kg/day)a | — | 0.0 ± 0.1 | 0.0 ± 0.1
Body weight (kg)a | 80 ± 15 | 81 ± 15 | 81 ± 15
Weight change from baseline | — | 0.8 ± 2.7 | 0.9 ± 2.6
Patients with severe hypoglycemia (n, %)b | — | 15 (2%) | 16 (2%)
a Values are Mean ± SD
b Severe hypoglycemia refers to hypoglycemia for which patients were not able to self-treat.

16 HOW SUPPLIED/STORAGE AND HANDLING

16.1 How Supplied

HUMALOG (insulin lispro) injection is a clear and colorless solution available as:

HUMALOG | Total Volume | Concentration | NDC Number | Package Size
U-100 multiple-dose vial | 10 mL | 100 units/mL | 0002-7510-01 | 1 vial
U-100 multiple-dose vial | 3 mL | 100 units/mL | 0002-7510-17 | 1 vial
U-100 multiple-dose vial | 3 mL | 100 units/mL | 0002-7533-01 | 1 vial
U-100 single-patient-use cartridge^1 | 3 mL | 100 units/mL | 0002-7516-59 | 5 cartridges
U-100 single-patient-use KwikPen | 3 mL | 100 units/mL | 0002-8799-59 | 5 pens
U-100 single-patient-use Tempo Pena | 3 mL | 100 units/mL | 0002-8213-05 | 5 pens
U-100 single-patient-use Junior KwikPen | 3 mL | 100 units/mL | 0002-7714-59 | 5 pens
U-200 single-patient-use KwikPen | 3 mL | 200 units/mL | 0002-7712-27 | 2 pens
U-200 single-patient-use Tempo Pena | 3 mL | 200 units/mL | 0002-8208-27 | 2 pens
a Tempo Pen contains a component that allows for data connectivity when used with a compatible transmitter.

The U-100 KwikPen, U-100 Tempo Pen, U-200 KwikPen, and U-200 Tempo Pen dial in 1-unit increments. The U-100 Junior KwikPen dials in 0.5-unit increments.

Each prefilled pen, cartridge, and reusable pen compatible with Lilly 3 mL cartridges is for single-patient-use only. HUMALOG prefilled pens, cartridges, and reusable pens compatible with Lilly 3 mL cartridges must never be shared between patients, even if the needle is changed. Patients using HUMALOG vials must never share needles or syringes with another person.

16.2 Storage and Handling

Dispense in the original sealed carton with the enclosed Instructions for Use.

Protect from direct heat and light. Do not freeze and do not use if it has been frozen.

See table below for storage information:

 | Not In-Use (Unopened) Room Temperature (Up to 86°F [30°C]) | Not In-Use (Unopened) Refrigerated (36° to 46°F [2° to 8°C]) | In-Use (Opened) (see temperature below)
HUMALOG U-100*
10 mL multiple-dose vial | 28 days | Until expiration date | 28 days Refrigerated or room temperature.
3 mL multiple-dose vial | 28 days | Until expiration date | 28 days Refrigerated or room temperature.
3 mL single-patient-use cartridge | 28 days | Until expiration date | 28 days Room temperature only (Do not refrigerate)
3 mL single-patient-use Humalog KwikPen | 28 days | Until expiration date | 28 days Room temperature only (Do not refrigerate)
3 mL single-patient-use Humalog Tempo Pen | 28 days | Until expiration date | 28 days Room temperature only (Do not refrigerate)
3 mL single-patient-use Humalog Junior KwikPen | 28 days | Until expiration date | 28 days Room temperature only (Do not refrigerate)
HUMALOG U-200*
3 mL single-patient-use Humalog KwikPen | 28 days | Until expiration date | 28 days Room temperature only (Do not refrigerate)
3 mL single-patient-use Humalog Tempo Pen | 28 days | Until expiration date | 28 days Room temperature only (Do not refrigerate)
* When stored at room temperature, HUMALOG U-100 and U-200 can only be used for a total of 28 days, including both not in-use (unopened) and in-use (opened) storage time.

Use in an External Insulin Pump — Change the HUMALOG U-100 in the reservoir at least every 7 days, or according to the pump user manual, whichever is shorter, or after exposure to temperatures that exceed 98.6°F (37°C).

Storage of Diluted HUMALOG U-100 for Subcutaneous Injection — Diluted HUMALOG for subcutaneous injection may be stored for 28 days when refrigerated at 41°F (5°C) and for 14 days at room temperature up to 86°F (30°C) [see Dosage and Administration (2.2)]. Do not dilute HUMALOG contained in a cartridge or HUMALOG used in an external insulin pump.

Storage of Intravenous Infusion Preparations with HUMALOG U-100

Intravenous infusion bags prepared with HUMALOG U-100 may be stored for 48 hours when refrigerated at 36° to 46°F (2° to 8°C). The prepared intravenous infusions bags may then be used at room temperature for up to an additional 48 hours [see Dosage and Administration (2.2)].

17 PATIENT COUNSELING INFORMATION

Advise the patient to read the FDA-approved patient labeling (Patient Information and Instructions for Use).

Never Share a HUMALOG Prefilled Pen, Cartridge, Reusable Pen Compatible with Lilly 3 mL Cartridges, or Syringe Between Patients

Advise patients that they must never share a HUMALOG prefilled pen, cartridge, or reusable pen compatible with Lilly 3 mL cartridges with another person, even if the needle is changed. Advise patients using HUMALOG vials not to share needles or syringes with another person. Sharing poses a risk for transmission of blood-borne pathogens [see Warnings and Precautions (5.1)].

Hyperglycemia or Hypoglycemia

Instruct patients on self-management procedures including glucose monitoring, proper injection technique, and management of hypoglycemia and hyperglycemia, especially at initiation of HUMALOG therapy. Instruct patients on handling of special situations such as intercurrent conditions (illness, stress, or emotional disturbances), an inadequate or skipped insulin dose, inadvertent administration of an increased insulin dose, inadequate food intake, and skipped meals. Instruct patients on the management of hypoglycemia.

Inform patients that their ability to concentrate and react may be impaired as a result of hypoglycemia. Advise patients who have frequent hypoglycemia or reduced or absent warning signs of hypoglycemia to use caution when driving or operating machinery [see Warnings and Precautions (5.3)].

Advise patients that changes in insulin regimen can predispose to hyperglycemia or hypoglycemia and that changes in insulin regimen should be made under close medical supervision [see Warnings and Precautions (5.2)].

Hypoglycemia due to Medication Errors

Instruct patients to always check the insulin container label before each injection to avoid mix-ups between insulin products [see Warnings and Precautions (5.4)].

Inform patients that HUMALOG U-200 contains 2 times as much insulin per mL as HUMALOG U-100. The HUMALOG U-200 prefilled pen dose window shows the number of units of HUMALOG U-200 to be injected so no dose conversion is required [see Dosage and Administration (2.1)].

Instruct patients to NOT transfer HUMALOG U-200 from the HUMALOG U-200 prefilled pen to a syringe. The markings on the syringe will not measure the dose correctly and this can result in overdosage and severe hypoglycemia. [see Warnings and Precautions (5.4)].

Hypersensitivity Reactions

Advise patients that hypersensitivity reactions have occurred with HUMALOG. Inform patients on the symptoms of hypersensitivity reactions [see Warnings and Precautions (5.5)].

Administration Instruction for HUMALOG U-200

Instruct patients to NOT mix HUMALOG U-200 with any other insulin.

Instructions For Patients Using Continuous Subcutaneous Insulin Pumps

- Do not use HUMALOG U-200 in a subcutaneous insulin pump.
- Train patients in intensive insulin therapy with multiple injections and in the function of their pump and pump accessories.
- Instruct patients to follow healthcare provider recommendations when setting pump basal rates and bolus settings.
- Refer to the continuous subcutaneous infusion pump user manual to see if HUMALOG can be used with the pump. See recommended reservoir and infusion sets in the insulin pump user manual.
- Instruct patients to replace insulin in the reservoir at least every 7 days, or according to the pump user manual, whichever is shorter; infusion sets and infusion set insertion sites should be changed in accordance with the manufacturers' user manual. By following this schedule, patients avoid insulin degradation, infusion set occlusion, and loss of the insulin preservative.
- Instruct patients to discard insulin exposed to temperatures higher than 98.6°F (37°C). The temperature of the insulin may exceed ambient temperature when the pump housing, cover, tubing or sport case is exposed to sunlight or radiant heat.
- Instruct patients to inform healthcare provider and select a new site for infusion if infusion site becomes erythematous, pruritic, or thickened.
- Instruct patients on the risk of rapid hyperglycemia and ketosis due to pump malfunction, infusion set occlusion, leakage, disconnection or kinking, and degraded insulin. Instruct patients on the risk of hypoglycemia from pump malfunction. If these problems cannot be promptly corrected, instruct patients to resume therapy with subcutaneous insulin injection and contact their healthcare provider [see Warnings and Precautions (5) and How Supplied/Storage and Handling (16.2)].

Manufactured by:
Eli Lilly and Company
Indianapolis, IN 46285, USA
US License Number 1891

^1 3 mL cartridge is for use in compatible insulin delivery devices, including HumaPen® Luxura® HD

Humalog®, Humalog KwikPen®, Humalog Tempo PenTM, Humalog® Junior KwikPen®, HumaPen®, HumaPen® Luxura® and HumaPen® Luxura® HD are trademarks of Eli Lilly and Company.

www.humalog.com
Copyright © 1996, 2025, Eli Lilly and Company. All rights reserved.

LOG-0012-USPI-20250507

Patient Package Insert

PATIENT INFORMATION
HUMALOG® (HU-ma-log)
(insulin lispro)
injection, for subcutaneous use

Do not share your HUMALOG prefilled pens, cartridges, reusable pen compatible with 3 mL cartridges of HUMALOG U-100, needles, or syringes with other people, even if the needle has been changed. You may give other people a serious infection or get a serious infection from them.
What is HUMALOG?

- HUMALOG is a rapid-acting man-made insulin used to control high blood sugar in adults and children with diabetes mellitus.

Who should not take HUMALOG?
Do not take HUMALOG if you:

- are having an episode of low blood sugar (hypoglycemia).
- have an allergy to insulin lispro or any of the ingredients in HUMALOG. See the end of this Patient Information leaflet for a complete list of ingredients in HUMALOG.

What should I tell my healthcare provider before taking HUMALOG?
Before taking HUMALOG, tell your healthcare provider about all your medical conditions, including if you:

- have liver or kidney problems.
- take any other medicines, especially ones called TZDs (thiazolidinediones).
- have heart failure or other heart problems. If you have heart failure, it may get worse while you take TZDs with HUMALOG.
- are pregnant or plan to become pregnant. Talk to your healthcare provider about the best way to control your blood sugar if you plan to become pregnant or while you are pregnant.
- are breastfeeding or plan to breastfeed. Talk with your healthcare provider about the best way to feed your baby while taking HUMALOG.

Tell your healthcare provider about all the medicines you take, including prescription and over-the-counter medicines, vitamins, and herbal supplements.
Before you start taking HUMALOG, talk to your healthcare provider about low blood sugar and how to manage it.

How should I use HUMALOG?

- Read the detailed Instructions for Use that comes with your HUMALOG.
- Take HUMALOG exactly as your healthcare provider tells you to. Your healthcare provider should tell you how much HUMALOG to take and when to take it.
- Know the type, strength and amount of insulin you take. Do not change the type or amount of insulin you take unless your healthcare provider tells you to. The amount of insulin and the best time for you to take your insulin may need to change if you take different types of insulin.
- Check your insulin label each time you give your injection to make sure you are taking the correct insulin.
- Always use a new needle for each injection to help prevent infections and blocked needles. Do not reuse or share your needles with other people. You may give other people a serious infection or get a serious infection from them.
- HUMALOG is a rapid-acting insulin. Inject HUMALOG within 15 minutes before or right after eating a meal.
- HUMALOG comes in U-100 (100 units/mL) and U-200 (200 units/mL) insulin strengths. HUMALOG U-200 contains 2 times as much insulin (200 units/mL) in 1 mL as HUMALOG U-100 (100 units/mL).
- HUMALOG U-100 comes in a vial, single-patient-use prefilled pens, or in a cartridge. HUMALOG U-200 comes in single-patient-use prefilled pens. Do not use a syringe to remove HUMALOG U-100 or HUMALOG U-200 from your single-patient-use prefilled pen or HUMALOG U-100 cartridge.
- The dose window on your HUMALOG U-100 or HUMALOG U-200 prefilled pen shows your dose of HUMALOG. Do not make any dose changes unless your healthcare provider tells you to.
- Inject HUMALOG U-100 or HUMALOG U-200 under the skin (subcutaneously) of your stomach area, buttocks, upper legs or upper arms
- HUMALOG U-100 can be given by continuous infusion under the skin (subcutaneously) through an insulin pump into an area of your body recommended in the instructions that come with your insulin pump. HUMALOG U-200 cannot be given through an insulin pump.
- HUMALOG U-100 can also be given in your vein (intravenously) by your healthcare provider. HUMALOG U-200 cannot be given in your vein.
- Change (rotate) your injection sites within the area you choose with each dose to reduce your risk of getting lipodystrophy (pits in skin or thickened skin) and localized cutaneous amyloidosis (skin with lumps) at the injection sites.
  - Do not use the exact same spot for each injection.
  - Do not inject where the skin has pits, is thickened, or has lumps.
  - Do not inject where the skin is tender, bruised, scaly or hard, or into scars or damaged skin.
- Do not mix HUMALOG U-100 in your insulin pump or the HUMALOG U-200 with any other type of insulin.
- Check your blood sugar levels. Ask your healthcare provider what your blood sugar should be and when you should check your blood sugar levels.

Keep HUMALOG and all medicines out of reach of children.

Your dose of HUMALOG may need to change because of a:

- change in physical activity or exercise, weight gain or loss, increased stress, illness, change in diet, or because of other medicines you take.

What should I avoid while using HUMALOG?
While using HUMALOG do not:

- drive or operate heavy machinery, until you know how HUMALOG affects you
- drink alcohol or take prescription or over-the-counter medicines that contain alcohol

What are the possible side effects of HUMALOG?
HUMALOG may cause serious side effects that can lead to death, including:

- low blood sugar (hypoglycemia). Signs and symptoms of low blood sugar may include:

- dizziness or light-headedness
- sweating
- confusion
- headache
- blurred vision

- slurred speech
- shakiness
- fast heartbeat
- anxiety, irritability or mood changes
- hunger

Your healthcare provider may prescribe a glucagon product for emergency use so that someone else can give you glucagon if your blood sugar becomes too low (severe hypoglycemia) and you are unable to take sugar by mouth.

- severe allergic reaction (whole body reaction). Get medical help right away, if you have any of these signs or symptoms of a severe allergic reaction:

- a rash over your whole body
- trouble breathing

- a fast heartbeat
- sweating

- low potassium in your blood (hypokalemia).
- heart failure. Taking certain diabetes pills called thiazolidinediones or “TZDs” with HUMALOG may cause heart failure in some people. This can happen even if you have never had heart failure or heart problems before. If you already have heart failure it may get worse while you take TZDs with HUMALOG. Your healthcare provider should monitor you closely while you are taking TZDs with HUMALOG. Tell your healthcare provider if you have any new or worse symptoms of heart failure including:

- shortness of breath
- swelling of your ankles or feet

- sudden weight gain

Treatment with TZDs and HUMALOG may need to be adjusted or stopped by your healthcare provider if you have new or worse heart failure.
Get emergency medical help if you have:

- trouble breathing
- shortness of breath
- fast heartbeat
- swelling of your face, tongue, or throat

- sweating
- extreme drowsiness
- dizziness
- confusion

The most common side effects of HUMALOG include:

- low blood sugar (hypoglycemia)
- reactions at your injection site
- skin thickening or pits at the injection site
  (lipodystrophy)

- weight gain
- swelling in your hands or feet
- itching
- rash

These are not all of the possible side effects of HUMALOG. Call your doctor for medical advice about side effects. You may report side effects to FDA at 1-800-FDA-1088.

General Information about the safe and effective use of HUMALOG.
Medicines are sometimes prescribed for purposes other than those listed in a Patient Information leaflet. Do not take HUMALOG for a condition for which it was not prescribed. Do not give HUMALOG to other people, even if they have the same symptoms that you have. It may harm them.
This Patient Information leaflet summarizes the most important information about the HUMALOG. If you would like more information, talk with your healthcare provider. You can ask your pharmacist or healthcare provider for information about HUMALOG that is written for health professionals.

What are the ingredients in HUMALOG U-100?
Active ingredient: insulin lispro
Inactive ingredients: dibasic sodium phosphate, glycerin, metacresol, trace amounts of phenol, zinc oxide (zinc ion), and Water for Injection, USP. Hydrochloric acid and/or sodium hydroxide is added to adjust the pH.

What are the ingredients in HUMALOG U-200?
Active ingredient: insulin lispro.
Inactive ingredient: glycerin, metacresol, trace amounts of phenol, tromethamine, zinc oxide (zinc ion), and Water for Injection, USP. Hydrochloric acid and/or sodium hydroxide is added to adjust the pH.
Humalog®, Humalog KwikPen®, and Humalog Tempo PenTM are trademarks of Eli Lilly and Company.
Manufactured by: Eli Lilly and Company, Indianapolis, IN 46285, USA, US License Number 1891
Copyright © 2015, 2025, Eli Lilly and Company. All rights reserved.
For more information, go to www.humalog.com or call 1-800-545-5979.

This Patient Information has been approved by the U.S. Food and Drug Administration

Revised: May 2025

LOG-0008-PPI-20250507

U-100 Vial Instructions for Use

INSTRUCTIONS FOR USE

HUMALOG® (HU-ma-log)
(insulin lispro)
injection, for subcutaneous use

3 mL or 10 mL multiple-dose vial (100 units per mL, U-100)

Read this Instructions for Use before you start taking HUMALOG and each time you get a new vial. There may be new information. This information does not take the place of talking to your healthcare provider about your medical condition or your treatment.

Do not share your needles or syringes with other people, even if the needle has been changed. You may give other people a serious infection or get a serious infection from them.

Supplies needed to give your injection

- a multiple-dose HUMALOG vial
- a U-100 insulin syringe and needle
- 2 alcohol swabs
- gauze
- 1 sharps container for throwing away used needles and syringes. See “Disposing of used needles and syringes” at the end of these instructions.

Vial

Syringe

Preparing your HUMALOG dose

- Wash your hands with soap and water.
- Check the HUMALOG label to make sure you are taking the right type of insulin. This is especially important if you use more than 1 type of insulin.
- HUMALOG should look clear and colorless. Do not use HUMALOG if it is thick, cloudy, or colored, or if you see lumps or particles in it.
- Do not use HUMALOG past the expiration date printed on the label or 28 days after you first use it.
- Always use a new syringe and needle for each injection to prevent infections and blocked needles. Do not reuse or share your syringes or needles with other people. You may give other people a serious infection or get a serious infection from them.

Step 1:
If you are using a new vial, pull off the plastic Protective Cap, but do not remove the Rubber Stopper.

Step 2:
Wipe the Rubber Stopper with an alcohol swab.

Step 3:
Remove the Needle Shield from the syringe by pulling the Needle Shield straight off. Hold the syringe with the needle pointing up. Pull down on the Plunger until the Plunger Tip reaches the line for the number of units for your prescribed dose.

(Example Dose: 20 units shown)

Step 4:
Push the needle through the Rubber Stopper of the vial.

Step 5:
Push the Plunger all the way in. This puts air into the vial.

Step 6:
Turn the vial and syringe upside down and slowly pull the Plunger down until the Plunger Tip is a few units past the line for your prescribed dose.

(Example Dose: 20 units
Plunger is shown at 24 units)

If there are air bubbles, tap the syringe gently a few times to let any air bubbles rise to the top.

Step 7:
Slowly push the Plunger up until the Plunger Tip reaches the line for your prescribed dose.
Check the syringe to make sure that you have the right dose.

(Example Dose: 20 units shown)

Step 8:
Pull the syringe out of the Rubber Stopper of the vial.

If you use HUMALOG with NPH insulin:

- NPH insulin is the only type of insulin that can be mixed with HUMALOG. Do not mix HUMALOG with any other type of insulin.
- HUMALOG should be drawn up into the syringe first, before you draw up your NPH insulin. Talk to your healthcare provider if you are not sure about the right way to mix HUMALOG and NPH insulin.
- Give your injection right away.

Giving your HUMALOG injection with a syringe

- Inject your insulin exactly as your healthcare provider has shown you. Your healthcare provider should tell you if you should pinch the skin before injecting.
- HUMALOG starts acting fast, so give your injection within 15 minutes before or right after you eat a meal.
- Change (rotate) your injection sites within the area you choose for each dose to reduce your risk of getting lipodystrophy (pits in skin or thickened skin) and localized cutaneous amyloidosis (skin with lumps) at the injection sites.
- Do not inject where the skin has pits, is thickened, or has lumps.
- Do not inject where the skin is tender, bruised, scaly or hard, or into scars or damaged skin.

Step 9:
Choose your injection site.
HUMALOG is injected under the skin (subcutaneously) of your stomach area (abdomen), buttocks, upper legs or upper arms.
Wipe the skin with an alcohol swab. Let the injection site dry before you inject your dose.

Step 10:
Insert the needle into your skin.

Step 11:
Push down on the Plunger to inject your dose.
The needle should stay in your skin for at least 5 seconds to make sure you have injected all of your insulin dose.

Step 12:
Pull the needle out of your skin.

- If you see blood after you take the needle out of your skin, press the injection site with a piece of gauze or an alcohol swab. Do not rub the area.
- Do not recap the needle. Recapping the needle can lead to a needle stick injury.

Giving your HUMALOG using an insulin pump

- HUMALOG should be given into an area of your body recommended in the instructions that come with your insulin pump.
- Change your infusion set and rotate the infusion set insertion site according to the manufacturer's user manual.
- Change (rotate) your insertion sites within the area you choose for each insertion to reduce your risk of getting lipodystrophy (pits in skin or thickened skin) and localized cutaneous amyloidosis (skin with lumps) at the insertion sites. Do not insert into the exact same spot for each insertion. Do not insert where the skin has pits, is thickened, or has lumps. Do not insert where the skin is tender, bruised, scaly or hard, or into scars or damaged skin.
- Change the insulin in the reservoir at least every 7 days or according to the pump user manual, whichever is shorter, even if you have not used all of the insulin.
- Do not dilute or mix HUMALOG with any other type of insulin in your insulin pump.
- See your insulin pump manual for instructions or talk to your healthcare provider.

Disposing of used needles and syringes

- Put your used needles and syringes in a FDA-cleared sharps disposal container right away after use. Do not throw away (dispose of) loose needles and syringes in your household trash.
- If you do not have a FDA-cleared sharps disposal container, you may use a household container that is:
  - made of a heavy-duty plastic,
  - can be closed with a tight-fitting, puncture-resistant lid, without sharps being able to come out,
  - upright and stable during use,
  - leak-resistant, and
  - properly labeled to warn of hazardous waste inside the container.
- When your sharps disposal container is almost full, you will need to follow your community guidelines for the right way to dispose of your sharps disposal container. There may be state or local laws about how you should throw away used needles and syringes. For more information about safe sharps disposal, and for specific information about sharps disposal in the state that you live in, go to the FDA's website at: http://www.fda.gov/safesharpsdisposal.
- Do not dispose of your used sharps disposal container in your household trash unless your community guidelines permit this. Do not recycle your used sharps disposal container.

How should I store HUMALOG?

All unopened vials:

- Store all unopened vials in the refrigerator at 36°F to 46°F (2°C to 8°C).
- Do not freeze. Do not use if HUMALOG has been frozen.
- Keep away from heat and out of direct light.
- Unopened vials can be used until the expiration date on the carton and label, if they have been stored in the refrigerator.
- Unopened vials should be thrown away after 28 days, if they are stored at room temperature.

After vials have been opened:

- Store opened vials in the refrigerator or at room temperature up to 86°F (30°C) for up to 28 days.
- Keep vials away from heat and out of direct light.
- Throw away all opened vials after 28 days of use, even if there is insulin left in the vial.

HUMALOG in an insulin pump:

- Throw away HUMALOG in the pump reservoir if it has been exposed to temperatures higher than 98.6°F (37°C).

Keep HUMALOG vials, syringes, needles and all medicines out of the reach of children.

If you have any questions or problems with your HUMALOG, contact Lilly at 1-800-Lilly-Rx (1-800-545-5979) or call your healthcare provider for help. For more information on HUMALOG and insulin, go to www.humalog.com.

Manufactured by:
Eli Lilly and Company
Indianapolis, IN 46285, USA
US License Number 1891

This Instructions for Use has been approved by the U.S. Food and Drug Administration.

Revised: July 2023

Scan this code to launch the humalog.com website

Humalog® is a registered trademark of Eli Lilly and Company.

Copyright © 1996, 2023, Eli Lilly and Company. All rights reserved.

LOGVL-0009-IFU-20230721

KwikPen U-100 Instructions for Use

INSTRUCTIONS FOR USE

HUMALOG (HU-ma-log) KwikPen®

(insulin lispro)

injection, for subcutaneous use

3 mL single-patient-use pen (100 units per mL)

Read the Instructions for Use before you start taking HUMALOG® and each time you get another KwikPen®. There may be new information. This information does not take the place of talking to your healthcare provider about your medical condition or your treatment.

Do not share your HUMALOG KwikPen with other people, even if the needle has been changed. You may give other people a serious infection or get a serious infection from them.

HUMALOG KwikPen (“Pen”) is a disposable single-patient-use prefilled pen containing 300 units of HUMALOG. You can give yourself more than 1 dose from the Pen. Each turn (click) of the Dose Knob dials 1 unit of insulin. You can give from 1 to 60 units in a single injection. If your dose is more than 60 units, you will need to give yourself more than 1 injection. The Plunger only moves a little with each injection, and you may not notice that it moves. The Plunger will only reach the end of the cartridge when you have used all 300 units in the Pen.

People who are blind or have vision problems should not use the Pen without help from a person trained to use the Pen.

How to recognize your HUMALOG KwikPen

- Pen color: Dark blue
- Dose Knob: Dark blue
- Labels: White label with burgundy stripe

Supplies you will need to give your injection

- HUMALOG KwikPen
- KwikPen compatible Needle (Becton, Dickinson and Company Pen Needles recommended)
- Alcohol swab
- Gauze

Preparing your Pen

- Wash your hands with soap and water.
- Check your Pen to make sure you are taking the right type of insulin. This is especially important if you use more than 1 type of insulin.
- Do not use your Pen past the expiration date printed on the Label or for more than 28 days after you first start using the Pen.
- Always use a new needle for each injection to help prevent infections and blocked needles. Do not reuse or share your needles with other people. You may give other people a serious infection or get a serious infection from them.

Step 1:

- Pull the Pen Cap straight off.
  - Do not remove the Pen Label.
- Wipe the Rubber Seal with an alcohol swab.

Step 2:

- Check the liquid in the Pen.
  HUMALOG should look clear and colorless. Do not use if it is cloudy, colored, or has particles or clumps in it.

Step 3:

- Select a new Needle.
- Pull off the Paper Tab from the Outer Needle Shield.

Step 4:

- Push the capped Needle straight onto the Pen and twist the Needle on until it is tight.

Step 5:

- Pull off the Outer Needle Shield. Do not throw it away.
- Pull off the Inner Needle Shield and throw it away.

Priming your Pen

Prime before each injection.

- Priming your Pen means removing the air from the Needle and Cartridge that may collect during normal use and ensures that the Pen is working correctly.
- If you do not prime before each injection, you may get too much or too little insulin.

Step 6:

- To prime your Pen, turn the Dose Knob to select 2 units.

Step 7:

- Hold your Pen with the Needle pointing up. Tap the Cartridge Holder gently to collect air bubbles at the top.

Step 8:

- Continue holding your Pen with Needle pointing up. Push the Dose Knob in until it stops, and “0” is seen in the Dose Window. Hold the Dose Knob in and count to 5 slowly.
  You should see insulin at the tip of the Needle.
  - If you do not see insulin, repeat priming steps 6 to 8, no more than 4 times.
  - If you still do not see insulin, change the Needle and repeat priming steps 6 to 8.

Small air bubbles are normal and will not affect your dose.

Selecting your dose

- You can give from 1 to 60 units in a single injection.
- If your dose is more than 60 units, you will need to give more than 1 injection.
  - If you need help with dividing up your dose the right way, ask your healthcare provider.
  - Use a new Needle for each injection and repeat the priming step.

Step 9:

- Turn the Dose Knob to select the number of units you need to inject. The Dose Indicator should line up with your dose.
  - The Pen dials 1 unit at a time.
  - The Dose Knob clicks as you turn it.
  - Do not dial your dose by counting the clicks. You may dial the wrong dose. This may lead to you getting too much insulin or not enough insulin.
  - The dose can be corrected by turning the Dose Knob in either direction until the correct dose lines up with the Dose Indicator.
  - The even numbers (for example, 12) are printed on the dial.
  - The odd numbers, (for example, 25) after the number 1, are shown as full lines.
- Always check the number in the Dose Window to make sure you have dialed the correct dose.

(Example: 12 units shown in the Dose Window)
(Example: 25 units shown in the Dose Window)

- The Pen will not let you dial more than the number of units left in the Pen.
- If you need to inject more than the number of units left in the Pen, you may either:
  - inject the amount left in your Pen and then use a new Pen to give the rest of your dose, or
  - get a new Pen and inject the full dose.
- It is normal to see a small amount of insulin left in the Pen that you can not inject.

Giving your injection

- Inject your insulin as your healthcare provider has shown you.
- Change (rotate) your injection sites within the area you choose for each dose to reduce your risk of getting lipodystrophy (pits in skin or thickened skin) and localized cutaneous amyloidosis (skin with lumps) at the injection sites.
- Do not inject where the skin has pits, is thickened, or has lumps.
- Do not inject where the skin is tender, bruised, scaly or hard, or into scars or damaged skin.
- Do not try to change your dose while injecting.

Step 10:

- Choose your injection site.
  HUMALOG is injected under the skin (subcutaneously) of your stomach area, buttocks, upper legs or upper arms.
- Wipe your skin with an alcohol swab, and let your skin dry before you inject your dose.

Step 11:

- Insert the Needle into your skin.
- Push the Dose Knob all the way in.
- Continue to hold the Dose Knob in and slowly count to 5 before removing the Needle.
  Do not try to inject your insulin by turning the Dose Knob. You will not receive your insulin by turning the Dose Knob.

Step 12:

- Pull the Needle out of your skin.
  A drop of insulin at the Needle tip is normal. It will not affect your dose.
- Check the number in the Dose Window.
  - If you see “0” in the Dose Window, you have received the full amount you dialed.
  - If you do not see “0” in the Dose Window, do not redial. Insert the Needle into your skin and finish your injection.
  - If you still do not think you received the full amount you dialed for your injection, do not start over or repeat the injection. Monitor your blood glucose as instructed by your healthcare provider.
  - If you normally need to give 2 injections for your full dose, be sure to give your second injection.

The Plunger only moves a little with each injection, and you may not notice that it moves.
If you see blood after you take the Needle out of your skin, press the injection site lightly with a piece of gauze or an alcohol swab. Do not rub the area.

After your injection

Step 13:

- Carefully replace the Outer Needle Shield.

Step 14:

- Unscrew the capped Needle and throw it away (see Disposing of Pens and Needles section).
- Do not store the Pen with the Needle attached to prevent leaking, blocking the Needle, and air from entering the Pen.

Step 15:

- Replace the Pen Cap by lining up the Cap Clip with the Dose Indicator and pushing straight on.

Disposing of Pens and Needles

- The used Pen may be discarded in your household trash after you have removed the needle.
- Put your used needles in a FDA-cleared sharps disposal container right away after use. Do not throw away (dispose of) loose needles in your household trash.
- If you do not have a FDA-cleared sharps disposal container, you may use a household container that is:
  - made of a heavy-duty plastic,
  - can be closed with a tight-fitting, puncture-resistant lid, without sharps being able to come out,
  - upright and stable during use,
  - leak-resistant, and
  - properly labeled to warn of hazardous waste inside the container.
- When your sharps disposal container is almost full, you will need to follow your community guidelines for the right way to dispose of your sharps disposal container. There may be state or local laws about how you should throw away used needles and syringes. For more information about safe sharps disposal, and for specific information about sharps disposal in the state that you live in, go to the FDA's website at: http://www.fda.gov/safesharpsdisposal
- Do not dispose of your used sharps disposal container in your household trash unless your community guidelines permit this. Do not recycle your used sharps disposal container.

Storing your Pen

Unused Pens

- Store unused Pens in the refrigerator at 36°F to 46°F (2°C to 8°C).
- Do not freeze your insulin. Do not use if it has been frozen.
- Unused Pens may be used until the expiration date printed on the Label, if the Pen has been kept in the refrigerator.

In-use Pen

- Store the Pen you are currently using at room temperature [up to 86°F (30°C)]. Keep away from heat and light.
- Throw away the HUMALOG Pen you are using after 28 days, even if it still has insulin left in it.

General information about the safe and effective use of your Pen

- Keep your Pen and needles out of the reach of children.
- Do not use your Pen if any part looks broken or damaged.
- Always carry an extra Pen in case yours is lost or damaged.

Troubleshooting

- If you can not remove the Pen Cap, gently twist the cap back and forth, and then pull the cap straight off.
- If the Dose Knob is hard to push:
  - Pushing the Dose Knob more slowly will make it easier to inject.
  - Your Needle may be blocked. Put on a new Needle and prime the Pen.
  - You may have dust, food, or liquid inside the Pen. Throw the Pen away and get a new Pen.

If you have any questions or problems with your HUMALOG KwikPen, contact Lilly at 1-800-LillyRx (1-800-545-5979) or call your healthcare provider for help. For more information on HUMALOG KwikPen and insulin, go to www.humalog.com.

Manufactured by:
Eli Lilly and Company
Indianapolis, IN 46285, USA
US License Number 1891

This Instructions for Use has been approved by the U.S. Food and Drug Administration.

Revised: July 2023

Scan this code to launch (www.humalog.com)

HUMALOG® and HUMALOG KwikPen® are registered trademarks of Eli Lilly and Company.

Copyright © 2007, 2023, Eli Lilly and Company. All rights reserved.

HUMALOG KwikPen meets the current dose accuracy and functional requirements of ISO 11608-1.

LOGKP-0009-IFU-20230721

Junior KwikPen U-100 Vial Instructions for Use

INSTRUCTIONS FOR USE

HUMALOG® (HU-ma-log) Junior KwikPen®

(insulin lispro)

injection, for subcutaneous use

3 mL single-patient-use pen (100 units per mL)

Read the Instructions for Use before you start taking HUMALOG and each time you get another HUMALOG® Junior KwikPen®. There may be new information. This information does not take the place of talking to your healthcare provider about your medical condition or your treatment.

Do not share your HUMALOG Junior KwikPen with other people, even if the needle has been changed. You may give other people a serious infection or get a serious infection from them.

HUMALOG Junior KwikPen (“Pen”) is a disposable single-patient-use prefilled pen containing 300 units of HUMALOG.

- You can give yourself more than 1 dose from the Pen.
- Each turn of the Dose Knob dials 0.5 (½) unit of insulin. You can give from 0.5 (½) to 30 units in a single injection.
- If your dose is more than 30 units, you will need to give yourself more than 1 injection.
- The Plunger only moves a little with each injection, and you may not notice that it moves. The Plunger will only reach the end of the cartridge when you have used all 300 units in the Pen.

People who are blind or have vision problems should not use the Pen without help from a person trained to use the Pen.

How to recognize your HUMALOG Junior KwikPen:

- Pen color: Blue
- Dose Knob: Blue, with raised ridges on end and side
- Label: White with an orange color bar and orange-to-yellow color band

Supplies needed to give your injection:

- HUMALOG Junior KwikPen
- KwikPen compatible Needle (BD [Becton, Dickinson and Company] Pen Needles recommended)
- Alcohol swab
- Gauze

Preparing your Pen

- Wash your hands with soap and water.
- Check the Pen to make sure you are taking the right type of insulin. This is especially important if you use more than 1 type of insulin.
- Do not use your Pen past the expiration date printed on the Label or for more than 28 days after you first start using the Pen.
- Always use a new needle for each injection to help prevent infections and blocked needles. Do not reuse or share your needles with other people. You may give other people a serious infection or get a serious infection from them.

Step 1:

- Pull the Pen Cap straight off.
  - Do not remove the Pen Label.
- Wipe the Rubber Seal with an alcohol swab.

Step 2:

- Check the liquid in the Pen.
  HUMALOG should look clear and colorless. Do not use if it is cloudy, colored, or has particles or clumps in it.

Step 3:

- Select a new Needle.
- Pull off the Paper Tab from the Outer Needle Shield.

Step 4:

- Push the capped Needle straight onto the Pen and twist the Needle on until it is tight.

Step 5:

- Pull off the Outer Needle Shield. Do not throw it away.
- Pull off the Inner Needle Shield and throw it away.

Priming your Pen

Prime before each injection.

- Priming your Pen means removing the air from the Needle and Cartridge that may collect during normal use and ensures that the Pen is working correctly.
- If you do not prime before each injection, you may get too much or too little insulin.

Step 6:

- To prime your Pen, turn the Dose Knob to select 2 units.

Step 7:

- Hold your Pen with the Needle pointing up. Tap the Cartridge Holder gently to collect air bubbles at the top.

Step 8:

- Continue holding your Pen with Needle pointing up. Push the Dose Knob in until it stops, and “0” is seen in the Dose Window. Hold the Dose Knob in and count to 5 slowly.
  You should see insulin at the tip of the Needle.
  - If you do not see insulin, repeat priming steps 6 to 8, no more than 4 times.
  - If you still do not see insulin, change the Needle and repeat priming steps 6 to 8.

Small air bubbles are normal and will not affect your dose.

Selecting your dose

- You can give from 0.5 (½) to 30 units in a single injection.
- If your dose is more than 30 units, you will need to give more than 1 injection.
  - If you need help with dividing up your dose the right way, ask your healthcare provider.
  - You must use a new Needle for each injection and repeat the priming step.

Step 9:

- Turn the Dose Knob to select the number of units you need to inject. The Dose Indicator should line up with your dose.
  - The Pen dials 0.5 (½) unit at a time.
  - The Dose Knob clicks as you turn it.
  - Do not dial your dose by counting the clicks. You may dial the wrong dose. This may lead to you getting too much insulin or not enough insulin.
  - The dose can be corrected by turning the Dose Knob in either direction until the correct dose lines up with the Dose Indicator.
  - The whole unit numbers (for example, 4) are printed on the dial.
  - The half units are shown as lines between the whole unit numbers.
- Always check the number in the Dose Window to make sure you have dialed the correct dose.

Example: 4 units shown in the Dose Window
Example: 10.5 (10 ½) units shown in the Dose Window

- The Pen will not let you dial more than the number of units left in the Pen.
- If you need to inject more than the number of units left in the Pen, you may either:
  - inject the amount left in your Pen and then use a new Pen to give the rest of your dose, or
  - get a new Pen and inject the full dose.
- It is normal to see a small amount of insulin left in the Pen that you can not inject.

Giving your injection

- Inject your insulin as your healthcare provider has shown you.
- Change (rotate) your injection sites within the area you choose for each dose to reduce your risk of getting lipodystrophy (pits in skin or thickened skin) and localized cutaneous amyloidosis (skin with lumps) at the injection sites.
- Do not inject where the skin has pits, is thickened, or has lumps.
- Do not inject where the skin is tender, bruised, scaly or hard, or into scars or damaged skin.
- Do not try to change your dose while injecting.

Step 10:

- Choose your injection site.
  HUMALOG is injected under the skin (subcutaneously) of your stomach area, buttocks, upper legs or upper arms.
- Wipe your skin with an alcohol swab, and let your skin dry before you inject your dose.

Step 11:

- Insert the Needle into your skin.
- Push the Dose Knob all the way in.

- Continue to hold the Dose Knob in and slowly count to 5 before removing the Needle.

Do not try to inject your insulin by turning the Dose Knob. You will not receive your insulin by turning the Dose Knob.

Step 12:

- Pull the Needle out of your skin.
  - A drop of insulin at the Needle tip is normal. It will not affect your dose.
- Check the number in the Dose Window
  - If you see “0” in the Dose window, you have received the full amount you dialed.
  - If you do not see “0” in the Dose window, do not redial. Insert the Needle into your skin and finish your injection.
  - If you still do not think you received the full amount you dialed for your injection, do not start over or repeat that injection. Monitor your blood glucose as instructed by your healthcare provider.
  - If you normally need to give 2 injections for your full dose, be sure to give your second injection.

The Plunger only moves a little with each injection and you may not notice that it moves.
If you see blood after you take the Needle out of your skin, press the injection site lightly with a piece of gauze or an alcohol swab. Do not rub the area.

After your injection

Step 13:

- Carefully replace the Outer Needle Shield.

Step 14:

- Unscrew the capped Needle and throw it away (see Disposing of Pens and Needles section).
- Do not store the Pen with the Needle attached to prevent leaking, blocking the Needle, and air from entering the Pen.

Step 15:

- Replace the Pen Cap by lining up the Cap Clip with the Dose Indicator and pushing straight on.

Disposing of Pens and Needles

- The used Pen may be discarded in your household trash after you have removed the needle.
- Put your used Needles in a FDA-cleared sharps disposal container right away after use. Do not throw away (dispose of) loose needles in your household trash.
- If you do not have a FDA-cleared sharps disposal container, you may use a household container that is:
  - made of a heavy-duty plastic,
  - can be closed with a tight-fitting, puncture-resistant lid, without sharps being able to come out,
  - upright and stable during use,
  - leak-resistant, and
  - properly labeled to warn of hazardous waste inside the container.
- When your sharps disposal container is almost full, you will need to follow your community guidelines for the right way to dispose of your sharps disposal container. There may be state or local laws about how you should throw away used needles. For more information about safe sharps disposal, and for specific information about sharps disposal in the state that you live in, go to the FDA's website at: http://www.fda.gov/safesharpsdisposal
- Do not dispose of your used sharps disposal container in your household trash unless your community guidelines permit this. Do not recycle the container.

Storing your Pen

Unused Pens

- Store unused Pens in the refrigerator at 36°F to 46°F (2°C to 8°C).
- Do not freeze your insulin. Do not use if it has been frozen.
- Unused Pens may be used until the expiration date printed on the Label, if the Pen has been kept in the refrigerator.

In-use Pen

- Store the Pen you are currently using at room temperature [up to 86°F (30°C)]. Keep away from heat and light.
- Throw away the HUMALOG Pen you are using after 28 days, even if it still has insulin left in it.

General information about the safe and effective use of your Pen

- Keep your Pen and Needles out of the sight and reach of children.
- Do not use your Pen if any part looks broken or damaged.
- Always carry an extra Pen in case yours is lost or damaged.

Troubleshooting

- If you can not remove the Pen Cap, gently twist the cap back and forth, and then pull the cap straight off.
- If the Dose Knob is hard to push:
  - Pushing the Dose Knob more slowly will make it easier to inject.
  - Your Needle may be blocked. Put on a new Needle and prime the Pen.
  - You may have dust, food, or liquid inside the Pen. Throw the Pen away and get a new Pen.

If you have any questions or problems with your HUMALOG Junior KwikPen, contact Lilly at 1-800-LillyRx (1-800-545-5979) or call your healthcare provider for help. For more information on HUMALOG Junior KwikPen and insulin, go to www.humalog.com.

Manufactured by:
Eli Lilly and Company
Indianapolis, IN 46285, USA
US License Number 1891

This Instructions for Use has been approved by the U.S. Food and Drug Administration.

Revised: July 2023

Scan this code to launch (www.humalog.com)

HUMALOG® and HUMALOG® Junior KwikPen® are trademarks of Eli Lilly and Company.

Copyright © 2017, 2023, Eli Lilly and Company. All rights reserved.

HUMALOG Junior KwikPen meets the current dose accuracy and functional requirements of ISO 11608-1.

LOGJRKP-0004-IFU-20230721

Tempo Pen U-100 Instructions for Use

INSTRUCTIONS FOR USE

HUMALOG® (HU-ma-log) Tempo Pen™

(insulin lispro)

injection, for subcutaneous use

3 mL single-patient-use pen, (100 units per mL)

Read the Instructions for Use before you start taking HUMALOG and each time you get another HUMALOG Tempo Pen. There may be new information. This information does not take the place of talking to your healthcare provider about your medical condition or your treatment.

Do not share your HUMALOG Tempo Pen with other people, even if the needle has been changed. You may give other people a serious infection or get a serious infection from them.

HUMALOG Tempo Pen (“Pen”) is a disposable single-patient-use prefilled pen containing 300 units of HUMALOG. You can give yourself more than 1 dose from the Pen. Each turn (click) of the Dose Knob dials 1 unit of insulin. You can give from 1 to 60 units in a single injection. If your dose is more than 60 units, you will need to give yourself more than 1 injection. The Plunger only moves a little with each injection, and you may not notice that it moves. The Plunger will only reach the end of the cartridge when you have used all 300 units in the Pen.

People who are blind or have vision problems should not use the Pen without help from a person trained to use the Pen.

This HUMALOG Tempo Pen contains a component that allows for data connectivity when used with a compatible transmitter.

How to recognize your HUMALOG Tempo Pen

- Pen color: Dark blue
- Dose Knob: Burgundy
- Labels: White label with burgundy stripe

Supplies you will need to give your injection

- HUMALOG Tempo Pen
- Tempo Pen compatible Needle (Becton, Dickinson and Company Pen Needles recommended)
- Alcohol swab
- Gauze

Preparing your Pen

- Wash your hands with soap and water.
- Check your Pen to make sure you are taking the right type of insulin. This is especially important if you use more than 1 type of insulin.
- Do not use your Pen past the expiration date printed on the Label or for more than 28 days after you first start using the Pen.
- Always use a new needle for each injection to help prevent infections and blocked needles. Do not reuse or share your needles with other people. You may give other people a serious infection or get a serious infection from them.

Step 1:

- Pull the Pen Cap straight off.
  - Do not remove the Pen Label.
- Wipe the Rubber Seal with an alcohol swab.

Step 2:

- Check the liquid in the Pen.
  HUMALOG should look clear and colorless. Do not use if it is cloudy, colored, or has particles or clumps in it.

Step 3:

- Select a new Needle.
- Pull off the Paper Tab from the Outer Needle Shield.

Step 4:

- Push the capped Needle straight onto the Pen and twist the Needle on until it is tight.

Step 5:

- Pull off the Outer Needle Shield. Do not throw it away.
- Pull off the Inner Needle Shield and throw it away.

Priming your Pen

Prime before each injection.

- Priming your Pen means removing the air from the Needle and Cartridge that may collect during normal use and ensures that the Pen is working correctly.
- If you do not prime before each injection, you may get too much or too little insulin.

Step 6:

- To prime your Pen, turn the Dose Knob to select 2 units.

Step 7:

- Hold your Pen with the Needle pointing up. Tap the Cartridge Holder gently to collect air bubbles at the top.

Step 8:

- Continue holding your Pen with the Needle pointing up. Push the Dose Knob in until it stops, and “0” is seen in the Dose Window. Hold the Dose Knob in and count to 5 slowly.
  You should see insulin at the tip of the Needle.
  - If you do not see insulin, repeat priming steps 6 to 8, but no more than 4 times.
  - If you still do not see insulin, change the Needle and repeat priming steps 6 to 8.

Small air bubbles are normal and will not affect your dose.

Selecting your dose

- You can give from 1 to 60 units in a single injection.
- If your dose is more than 60 units, you will need to give more than 1 injection.
  - If you need help with dividing up your dose the right way, ask your healthcare provider.
  - Use a new Needle for each injection and repeat the priming step.

Step 9:; - Turn the Dose Knob to select the number of units you need to inject. The Dose Indicator should line up with your dose. - The Pen dials 1 unit at a time. - The Dose Knob clicks as you turn it. - Do not dial your dose by counting the clicks. You may dial the wrong dose. This may lead to you getting too much insulin or not enough insulin. - The dose can be corrected by turning the Dose Knob in either direction until the correct dose lines up with the Dose Indicator. - The even numbers (for example, 12) are printed on the dial. - The odd numbers, (for example, 25) after the number 1, are shown as full lines. - Always check the number in the Dose Window to make sure you have dialed the correct dose.
Step 9:; - Turn the Dose Knob to select the number of units you need to inject. The Dose Indicator should line up with your dose. - The Pen dials 1 unit at a time. - The Dose Knob clicks as you turn it. - Do not dial your dose by counting the clicks. You may dial the wrong dose. This may lead to you getting too much insulin or not enough insulin. - The dose can be corrected by turning the Dose Knob in either direction until the correct dose lines up with the Dose Indicator. - The even numbers (for example, 12) are printed on the dial. - The odd numbers, (for example, 25) after the number 1, are shown as full lines. - Always check the number in the Dose Window to make sure you have dialed the correct dose. | (Example: 12 units shown in the Dose Window)
Step 9:; - Turn the Dose Knob to select the number of units you need to inject. The Dose Indicator should line up with your dose. - The Pen dials 1 unit at a time. - The Dose Knob clicks as you turn it. - Do not dial your dose by counting the clicks. You may dial the wrong dose. This may lead to you getting too much insulin or not enough insulin. - The dose can be corrected by turning the Dose Knob in either direction until the correct dose lines up with the Dose Indicator. - The even numbers (for example, 12) are printed on the dial. - The odd numbers, (for example, 25) after the number 1, are shown as full lines. - Always check the number in the Dose Window to make sure you have dialed the correct dose. | (Example: 25 units shown in the Dose Window)

- The Pen will not let you dial more than the number of units left in the Pen.
- If you need to inject more than the number of units left in the Pen, you may either:
  - inject the amount left in your Pen and then use a new Pen to give the rest of your dose, or
  - get a new Pen and inject the full dose.
- It is normal to see a small amount of insulin left in the Pen that you cannot inject.

Giving your injection

- Inject your insulin as your healthcare provider has shown you.
- Change (rotate) your injection sites within the area you choose for each dose to reduce your risk of getting lipodystrophy (pits in skin or thickened skin) and localized cutaneous amyloidosis (skin with lumps) at the injection sites.
- Do not inject where the skin has pits, is thickened, or has lumps.
- Do not inject where the skin is tender, bruised, scaly or hard, or into scars or damaged skin.
- Do not try to change your dose while injecting.

Step 10:

- Choose your injection site.
  HUMALOG is injected under the skin (subcutaneously) of your stomach area, buttocks, upper legs or upper arms.
- Wipe your skin with an alcohol swab, and let your skin dry before you inject your dose.

Step 11:
Insert the Needle into your skin.
Push the Dose Knob all the way in.
Continue to hold the Dose Knob in and slowly count to 5 before removing the Needle.
Do not try to inject your insulin by turning the Dose Knob. You will not receive your insulin by turning the Dose Knob.

Step 12:

- Pull the Needle out of your skin.
  A drop of insulin at the Needle tip is normal. It will not affect your dose.
- Check the number in the Dose Window.
  - If you see “0” in the Dose Window, you have received the full amount you dialed.
  - If you do not see “0” in the Dose Window, do not redial. Insert the Needle into your skin and finish your injection.
  - If you still do not think you received the full amount you dialed for your injection, do not start over or repeat the injection. Monitor your blood sugar (glucose) as instructed by your healthcare provider.
  - If you normally need to give 2 injections for your full dose, be sure to give your second injection.

The Plunger only moves a little with each injection, and you may not notice that it moves.
If you see blood after you take the Needle out of your skin, press the injection site lightly with a piece of gauze or an alcohol swab. Do not rub the area.

After your injection

Step 13:

- Carefully replace the Outer Needle Shield.

Step 14:

- Unscrew the capped Needle and throw it away (see Disposing of Pens and Needles section).
- Do not store the Pen with the Needle attached to prevent leaking, blocking the Needle, and air from entering the Pen.

Step 15:

- Replace the Pen Cap by lining up the Cap Clip with the Dose Indicator and pushing straight on.

Disposing of Pens and Needles

- The used Pen may be discarded in your household trash after you have removed the needle.
- Put your used needles in a FDA-cleared sharps disposal container right away after use. Do not throw away (dispose of) loose needles in your household trash.
- If you do not have a FDA-cleared sharps disposal container, you may use a household container that is:
  - made of a heavy-duty plastic,
  - can be closed with a tight-fitting, puncture-resistant lid, without sharps being able to come out,
  - upright and stable during use,
  - leak-resistant, and
  - properly labeled to warn of hazardous waste inside the container.
- When your sharps disposal container is almost full, you will need to follow your community guidelines for the right way to dispose of your sharps disposal container. There may be state or local laws about how you should throw away used needles and syringes. For more information about safe sharps disposal, and for specific information about sharps disposal in the state that you live in, go to the FDA's website at: http://www.fda.gov/safesharpsdisposal
- Do not dispose of your used sharps disposal container in your household trash unless your community guidelines permit this. Do not recycle your used sharps disposal container.

Storing your Pen

Unopened Pens

- Store unopened Pens in the refrigerator at 36°F to 46°F (2°C to 8°C).
- Do not freeze your insulin. Do not use if it has been frozen.
- Unopened Pens may be used until the expiration date printed on the Label, if the Pen has been kept in the refrigerator.

In-use Pen

- Store the Pen you are currently using at room temperature [up to 86°F (30°C)]. Keep away from heat and light.
- Throw away the HUMALOG Tempo Pen you are using after 28 days, even if it still has insulin left in it.

General information about the safe and effective use of your Pen

- Keep your Pen and needles out of the reach of children.
- Do not use your Pen if any part looks broken or damaged.
- Always carry an extra Pen in case yours is lost or damaged.

Troubleshooting

- If you cannot remove the Pen Cap, gently twist the cap back and forth, and then pull the cap straight off.
- If the Dose Knob is hard to push:
  - Pushing the Dose Knob more slowly will make it easier to inject.
  - Your Needle may be blocked. Put on a new Needle and prime the Pen.
  - You may have dust, food, or liquid inside the Pen. Throw the Pen away and get a new Pen.

If you have any questions or problems with your HUMALOG Tempo Pen, contact Lilly at 1-800-LillyRx (1-800-545-5979) or call your healthcare provider for help. For more information on HUMALOG Tempo Pen and insulin, go to www.humalog.com.

Manufactured by:
Eli Lilly and Company
Indianapolis, IN 46285, USA
US License Number 1891

This Instructions for Use has been approved by the U.S. Food and Drug Administration.

Revised: July 2023

Scan this code to launch (www.humalog.com)

HUMALOG® is a registered trademark and TEMPO PENTM is a trademark of Eli Lilly and Company.

Copyright © 2019, 2023, Eli Lilly and Company. All rights reserved.

HUMALOG Tempo Pen meets the current dose accuracy and functional requirements of ISO 11608-1.

LOGTP-0002-IFU-20230721

KwikPen U-200 Instructions for Use

INSTRUCTIONS FOR USE

HUMALOG (HU-ma-log) KwikPen®

(insulin lispro)

injection, for subcutaneous use

3 mL single-patient-use pen (200 units per mL)

Read the Instructions for Use before you start taking HUMALOG® and each time you get another KwikPen®. There may be new information. This information does not take the place of talking to your healthcare provider about your medical condition or your treatment.

Do not share your HUMALOG KwikPen with other people, even if the needle has been changed. You may give other people a serious infection or get a serious infection from them.

HUMALOG KwikPen 200 units/mL (“Pen”) is a disposable single-patient-use prefilled pen containing 600 units of HUMALOG. You can give yourself more than 1 dose from the Pen. Each turn (click) of the Dose Knob dials 1 unit of insulin. You can give from 1 to 60 units in a single injection. If your dose is more than 60 units, you will need to give yourself more than 1 injection. The Plunger only moves a little with each injection, and you may not notice that it moves. The Plunger will only reach the end of the cartridge when you have used all 600 units in the Pen.

Inject HUMALOG 200 units/mL only with your Pen. Do not transfer insulin from your Pen to a syringe. Syringes will not measure 200 units/mL insulin correctly. A severe overdose can result, causing very low blood sugar which may put your life in danger.

People who are blind or have vision problems should not use the Pen without help from a person trained to use the Pen.

How to recognize your HUMALOG 200 units/mL KwikPen

- Pen color: Dark grey
- Dose Knob: Dark grey with burgundy ring on the end
- Label: Burgundy label with “200 units per mL (U-200)” in white stripe and a grey and burgundy checker board design.

Supplies needed to give your injection

- HUMALOG KwikPen
- KwikPen compatible Needle (Becton, Dickinson and Company Pen Needles recommended)
- Alcohol swab
- Gauze

Preparing your Pen

- Wash your hands with soap and water.
- Check your Pen to make sure you are taking the right type of insulin. This is especially important if you use more than 1 type of insulin.
- Do not use your Pen past the expiration date printed on the Label or for more than 28 days after you first start using the Pen.
- Always use a new needle for each injection to help prevent infections and blocked needles. Do not reuse or share your needles with other people. You may give other people a serious infection or get a serious infection from them.

Step 1:

- Pull the Pen Cap straight off.
  - Do not remove the Pen Label.
- Wipe the Rubber Seal with an alcohol swab.

Step 2:

- Check the liquid in the Pen.
  HUMALOG should look clear and colorless. Do not use if it is cloudy, colored, or has particles or clumps in it.

Step 3:

- Select a new Needle.
- Pull off the Paper Tab from the Outer Needle Shield.

Step 4:

- Push the capped Needle straight onto the Pen and twist the Needle on until it is tight.

Step 5:

- Pull off the Outer Needle Shield. Do not throw it away.
- Pull off the Inner Needle Shield and throw it away.

Priming your Pen

Prime before each injection.

- Priming your Pen means removing the air from the Needle and Cartridge that may collect during normal use and ensures that the Pen is working correctly.
- If you do not prime before each injection, you may get too much or too little insulin.

Step 6:

- To prime your Pen, turn the Dose Knob to select 2 units.

Step 7:

- Hold your Pen with the Needle pointing up. Tap the Cartridge Holder gently to collect air bubbles at the top.

Step 8:

- Continue holding your Pen with Needle pointing up. Push the Dose Knob in until it stops, and “0” is seen in the Dose Window. Hold the Dose Knob in and count to 5 slowly.
  You should see insulin at the tip of the Needle.
  - If you do not see insulin, repeat priming steps 6 to 8, no more than 8 times.
  - If you still do not see insulin, change the Needle and repeat priming steps 6 to 8.

Small air bubbles are normal and will not affect your dose.

Selecting your dose

This Pen has been made to deliver the dose that is shown in the Dose Window. Dial your usual dose as instructed by your healthcare provider.

- You can give from 1 to 60 units in a single injection.
- If your dose is more than 60 units, you will need to give more than 1 injection.
  - If you need help with dividing up your dose the right way, ask your healthcare provider.
  - Use a new Needle for each injection and repeat the priming step.

Step 9:

- Turn the Dose Knob to select the number of units you need to inject. The Dose Indicator should line up with your dose.
  - The Pen dials 1 unit at a time.
  - The Dose Knob clicks as you turn it.
  - Do not dial your dose by counting the clicks. You may dial the wrong dose. This may lead to you getting to much insulin or not enough insulin.
  - The dose can be corrected by turning the Dose Knob in either direction until the correct dose lines up with the Dose Indicator.
  - The even numbers (for example, 12) are printed on the dial.
  - The odd numbers, (for example, 25) after the number 1, are shown as full lines.
- Always check the number in the Dose Window to make sure you have dialed the correct dose.

(Example: 12 units shown in the Dose Window)
(Example: 25 units shown in the Dose Window)

- The Pen will not let you dial more than the number of units left in the Pen.
- If you need to inject more than the number of units left in the Pen, you may either:
  - inject the amount left in your Pen and then use a new Pen to give the rest of your dose,
    or
  - get a new Pen and inject the full dose.
- It is normal to see a small amount of insulin left in the Pen that you can not inject. Do not transfer this to a syringe. Severe overdose can result.

Giving your injection

- Inject your insulin as your healthcare provider has shown you.
- Change (rotate) your injection sites within the area you choose for each dose to reduce your risk of getting lipodystrophy (pits in skin or thickened skin) and localized cutaneous amyloidosis (skin with lumps) at the injection sites.
- Do not use the exact same spot for each injection.
- Do not inject where the skin has pits, is thickened, or has lumps.
- Do not inject where the skin is tender, bruised, scaly or hard, or into scars or damaged skin.
- Do not try to change your dose while injecting.

Step 10:

- Choose your injection site.
  HUMALOG is injected under the skin (subcutaneously) of your stomach area, buttocks, upper legs or upper arms.
- Wipe your skin with an alcohol swab, and let your skin dry before you inject your dose.

Step 11:

- Insert the Needle into your skin.
- Push the Dose Knob all the way in.

- Continue to hold the Dose Knob in and slowly count to 5 before removing the Needle.

Do not try to inject your insulin by turning the Dose Knob. You will not receive your insulin by turning the Dose Knob.

Step 12:

- Pull the Needle out of your skin.
  - A drop of insulin at the Needle tip is normal. It will not affect your dose.
- Check the number in the Dose Window
  - If you see “0” in the Dose Window, you have received the full amount you dialed.
  - If you do not see “0” in the Dose Window, do not redial. Insert the Needle into your skin and finish your injection.
  - If you still do not think you received the full amount you dialed for your injection, do not start over or repeat the injection. Monitor your blood glucose as instructed by your healthcare provider.
  - If you normally need to give 2 injections for your full dose, be sure to give your second injection.

The Plunger only moves a little with each injection, and you may not notice that it moves.
If you see blood after you take the Needle out of your skin, press the injection site lightly with a piece of gauze or an alcohol swab. Do not rub the area.

After your injection

Step 13:

- Carefully replace the Outer Needle Shield.

Step 14:

- Unscrew the capped Needle and throw it away (see Disposing of Pens and Needles section).
- Do not store the Pen with the Needle attached to prevent leaking, blocking the Needle, and air from entering the Pen.

Step 15:

- Replace the Pen Cap by lining up the Cap Clip with the Dose Indicator and pushing straight on.

Disposing of Pens and Needles

- The used Pen may be discarded in your household trash after you have removed the needle.
- Put your used needles in a FDA-cleared sharps disposal container right away after use. Do not throw away (dispose of) loose needles in your household trash.
- If you do not have a FDA-cleared sharps disposal container, you may use a household container that is:
  - made of a heavy-duty plastic,
  - can be closed with a tight-fitting, puncture-resistant lid, without sharps being able to come out,
  - upright and stable during use,
  - leak-resistant, and
  - properly labeled to warn of hazardous waste inside the container.
- When your sharps disposal container is almost full, you will need to follow your community guidelines for the right way to dispose of your sharps disposal container. There may be state or local laws about how you should throw away used needles and syringes. For more information about safe sharps disposal, and for specific information about sharps disposal in the state that you live in, go to the FDA's website at: http://www.fda.gov/safesharpsdisposal
- Do not dispose of your used sharps disposal container in your household trash unless your community guidelines permit this. Do not recycle your used sharps disposal container.

Storing your Pen

Unused Pens

- Store unused Pens in the refrigerator at 36°F to 46°F (2°C to 8°C).
- Do not freeze your insulin. Do not use if it has been frozen.
- Unused Pens may be used until the expiration date printed on the Label, if the Pen has been kept in the refrigerator.

In-use Pen

- Store the Pen you are currently using at room temperature [up to 86°F (30°C)]. Keep away from heat and light.
- Throw away the HUMALOG Pen you are using after 28 days, even if it still has insulin left in it.

General information about the safe and effective use of your Pen

- Keep your Pen and needles out of the sight and reach of children.
- Do not use your Pen if any part looks broken or damaged.
- Always carry an extra Pen in case yours is lost or damaged.

Troubleshooting

- If you can not remove the Pen Cap, gently twist the cap back and forth, and then pull the cap straight off.
- If the Dose Knob is hard to push:
  - Pushing the Dose Knob more slowly will make it easier to inject.
  - Your Needle may be blocked. Put on a new Needle and prime the Pen.
  - You may have dust, food, or liquid inside the Pen. Throw the Pen away and get a new Pen.

If you have any questions or problems with your HUMALOG KwikPen, contact Lilly at 1-800-LillyRx (1-800-545-5979) or call your healthcare provider for help. For more information on HUMALOG KwikPen and insulin, go to www.humalog.com.

Manufactured by:
Eli Lilly and Company
Indianapolis, IN 46285, USA
US License Number 1891

This Instructions for Use has been approved by the U.S. Food and Drug Administration.

Revised: July 2023

Scan this code to launch (www.humalog.com)

HUMALOG® and HUMALOG KwikPen® are trademarks of Eli Lilly and Company.

Copyright © 2015, 2023, Eli Lilly and Company. All rights reserved.

HUMALOG KwikPen meets the current dose accuracy and functional requirements of ISO 11608-1.

LOGKP200-0005-IFU-20230721

Tempo Pen U-200 Instructions for Use

INSTRUCTIONS FOR USE

HUMALOG® (HU-ma-log) Tempo Pen™

(insulin lispro)

injection, for subcutaneous use

3 mL single-patient-use pen (200 units per mL)

Read the Instructions for Use before you start taking HUMALOG and each time you get another Tempo Pen There may be new information. This information does not take the place of talking to your healthcare provider about your medical condition or your treatment.

Do not share your HUMALOG Tempo Pen with other people, even if the needle has been changed. You may give other people a serious infection or get a serious infection from them.

HUMALOG Tempo Pen 200 units/mL (“Pen”) is a disposable single-patient-use prefilled pen containing 600 units of HUMALOG. You can give yourself more than 1 dose from the Pen. Each turn (click) of the Dose Knob dials 1 unit of insulin. You can give from 1 to 60 units in a single injection. If your dose is more than 60 units, you will need to give yourself more than 1 injection. The Plunger only moves a little with each injection, and you may not notice that it moves. The Plunger will only reach the end of the cartridge when you have used all 600 units in the Pen.

Do not transfer insulin from your Pen to a syringe. Syringes will not measure 200 units/mL insulin correctly. A severe overdose can result, causing very low blood sugar which may put your life in danger.

People who are blind or have vision problems should not use the Pen without help from a person trained to use the Pen.

This HUMALOG Tempo Pen contains a component that allows for data connectivity when used with a compatible transmitter.

How to recognize your HUMALOG 200 units/mL Tempo Pen

- Pen color: Dark grey
- Dose Knob: Red
- Label: Burgundy label with "200 units per mL (U-200)" in white stripe and a grey and burgundy checker board design.

Supplies needed to give your injection

- HUMALOG Tempo Pen
- Tempo Pen compatible Needle (Becton, Dickinson and Company Pen Needles recommended)
- Alcohol swab
- Gauze

Preparing your Pen

- Wash your hands with soap and water.
- Check your Pen to make sure you are taking the right type of insulin. This is especially important if you use more than 1 type of insulin.
- Do not use your Pen past the expiration date printed on the Label or for more than 28 days after you first start using the Pen.
- Always use a new needle for each injection to help prevent infections and blocked needles. Do not reuse or share your needles with other people. You may give other people a serious infection or get a serious infection from them.

Step 1:

- Pull the Pen Cap straight off.
  - Do not remove the Pen Label.
- Wipe the Rubber Seal with an alcohol swab.

Step 2:

- Check the liquid in the Pen.
  HUMALOG should look clear and colorless. Do not use if it is cloudy, colored, or has particles or clumps in it.

Step 3:

- Select a new Needle.
- Pull off the Paper Tab from the Outer Needle Shield.

Step 4:

- Push the capped Needle straight onto the Pen and twist the Needle on until it is tight.

Step 5:

- Pull off the Outer Needle Shield. Do not throw it away.
- Pull off the Inner Needle Shield and throw it away.

Priming your Pen

Prime before each injection.

- Priming your Pen means removing the air from the Needle and Cartridge that may collect during normal use and ensures that the Pen is working correctly.
- If you do not prime before each injection, you may get too much or too little insulin.

Step 6:

- To prime your Pen, turn the Dose Knob to select 2 units.

Step 7:

- Hold your Pen with the Needle pointing up. Tap the Cartridge Holder gently to collect air bubbles at the top.

Step 8:

- Continue holding your Pen with Needle pointing up. Push the Dose Knob in until it stops, and “0” is seen in the Dose Window. Hold the Dose Knob in and count to 5 slowly.
  You should see insulin at the tip of the Needle.
  - If you do not see insulin, repeat priming steps 6 to 8, no more than 8 times.
  - If you still do not see insulin, change the Needle and repeat priming steps 6 to 8.

Small air bubbles are normal and will not affect your dose.

Selecting your dose

This Pen has been made to deliver the dose that is shown in the Dose Window. Dial your usual dose as instructed by your healthcare provider.

- You can give from 1 to 60 units in a single injection.
- If your dose is more than 60 units, you will need to give more than 1 injection.
  - If you need help with dividing up your dose the right way, ask your healthcare provider.
  - Use a new Needle for each injection and repeat the priming step.

Step 9:; - Turn the Dose Knob to select the number of units you need to inject. The Dose Indicator should line up with your dose. - The Pen dials 1 unit at a time. - The Dose Knob clicks as you turn it. - Do not dial your dose by counting the clicks. You may dial the wrong dose. This may lead to you getting too much insulin or not enough insulin. - The dose can be corrected by turning the Dose Knob in either direction until the correct dose lines up with the Dose Indicator. - The even numbers (for example, 12) are printed on the dial. - The odd numbers, (for example, 25) after the number 1, are shown as full lines. - Always check the number in the Dose Window to make sure you have dialed the correct dose.
Step 9:; - Turn the Dose Knob to select the number of units you need to inject. The Dose Indicator should line up with your dose. - The Pen dials 1 unit at a time. - The Dose Knob clicks as you turn it. - Do not dial your dose by counting the clicks. You may dial the wrong dose. This may lead to you getting too much insulin or not enough insulin. - The dose can be corrected by turning the Dose Knob in either direction until the correct dose lines up with the Dose Indicator. - The even numbers (for example, 12) are printed on the dial. - The odd numbers, (for example, 25) after the number 1, are shown as full lines. - Always check the number in the Dose Window to make sure you have dialed the correct dose. | (Example: 12 units shown in the Dose Window)
Step 9:; - Turn the Dose Knob to select the number of units you need to inject. The Dose Indicator should line up with your dose. - The Pen dials 1 unit at a time. - The Dose Knob clicks as you turn it. - Do not dial your dose by counting the clicks. You may dial the wrong dose. This may lead to you getting too much insulin or not enough insulin. - The dose can be corrected by turning the Dose Knob in either direction until the correct dose lines up with the Dose Indicator. - The even numbers (for example, 12) are printed on the dial. - The odd numbers, (for example, 25) after the number 1, are shown as full lines. - Always check the number in the Dose Window to make sure you have dialed the correct dose. | (Example: 25 units shown in the Dose Window)

- The Pen will not let you dial more than the number of units left in the Pen.
- If you need to inject more than the number of units left in the Pen, you may either:
  - inject the amount left in your Pen and then use a new Pen to give the rest of your dose, or
  - get a new Pen and inject the full dose.
- It is normal to see a small amount of insulin left in the Pen that you cannot inject. Do not transfer this to a syringe. Severe overdose can result.

Giving your injection

- Inject your insulin as your healthcare provider has shown you.
- Change (rotate) your injection sites within the area you choose for each dose to reduce your risk of getting lipodystrophy (pits in skin or thickened skin) and localized cutaneous amyloidosis (skin with lumps) at the injection sites.
- Do not use the exact same spot for each injection.
- Do not inject where the skin has pits, is thickened, or has lumps.
- Do not inject where the skin is tender, bruised, scaly or hard, or into scars or damaged skin.
- Do not try to change your dose while injecting.

Step 10:

- Choose your injection site.
  HUMALOG is injected under the skin (subcutaneously) of your stomach area, buttocks, upper legs or upper arms.
- Wipe your skin with an alcohol swab, and let your skin dry before you inject your dose.

Step 11:

- Insert the Needle into your skin.
- Push the Dose Knob all the way in.
- Continue to hold the Dose Knob in and slowly count to 5 before removing the Needle.

Do not try to inject your insulin by turning the Dose Knob. You will not receive your insulin by turning the Dose Knob.

Step 12:

- Pull the Needle out of your skin.
  - A drop of insulin at the Needle tip is normal. It will not affect your dose.
- Check the number in the Dose Window
  - If you see “0” in the Dose Window, you have received the full amount you dialed.
  - If you do not see “0” in the Dose Window, do not redial. Insert the Needle into your skin and finish your injection.
  - If you still do not think you received the full amount you dialed for your injection, do not start over or repeat the injection. Monitor your blood sugar (glucose) as instructed by your healthcare provider.
  - If you normally need to give 2 injections for your full dose, be sure to give your second injection.

The Plunger only moves a little with each injection, and you may not notice that it moves.
If you see blood after you take the Needle out of your skin, press the injection site lightly with a piece of gauze or an alcohol swab. Do not rub the area.

After your injection

Step 13:

- Carefully replace the Outer Needle Shield.

Step 14:

- Unscrew the capped Needle and throw it away (see Disposing of Pens and Needles section).
- Do not store the Pen with the Needle attached to prevent leaking, blocking the Needle, and air from entering the Pen.

Step 15:

- Replace the Pen Cap by lining up the Cap Clip with the Dose Indicator and pushing straight on.

Disposing of Pens and Needles

- The used Pen may be discarded in your household trash after you have removed the needle.
- Put your used needles in a FDA-cleared sharps disposal container right away after use. Do not throw away (dispose of) loose needles in your household trash.
- If you do not have a FDA-cleared sharps disposal container, you may use a household container that is:
  - made of a heavy-duty plastic,
  - can be closed with a tight-fitting, puncture-resistant lid, without sharps being able to come out,
  - upright and stable during use,
  - leak-resistant, and
  - properly labeled to warn of hazardous waste inside the container.
- When your sharps disposal container is almost full, you will need to follow your community guidelines for the right way to dispose of your sharps disposal container. There may be state or local laws about how you should throw away used needles and syringes. For more information about safe sharps disposal, and for specific information about sharps disposal in the state that you live in, go to the FDA's website at: http://www.fda.gov/safesharpsdisposal
- Do not dispose of your used sharps disposal container in your household trash unless your community guidelines permit this. Do not recycle your used sharps disposal container.

Storing your Pen

Unused Pens

- Store unused Pens in the refrigerator at 36°F to 46°F (2°C to 8°C).
- Do not freeze your insulin. Do not use if it has been frozen.
- Unused Pens may be used until the expiration date printed on the Label, if the Pen has been kept in the refrigerator.

In-use Pen

- Store the Pen you are currently using at room temperature [up to 86°F (30°C)]. Keep away from heat and light.
- Throw away the HUMALOG Tempo Pen you are using after 28 days, even if it still has insulin left in it.

General information about the safe and effective use of your Pen

- Keep your Pen and needles out of the sight and reach of children.
- Do not use your Pen if any part looks broken or damaged.
- Always carry an extra Pen in case yours is lost or damaged.

Troubleshooting

- If you cannot remove the Pen Cap, gently twist the cap back and forth, and then pull the cap straight off.
- If the Dose Knob is hard to push:
  - Pushing the Dose Knob more slowly will make it easier to inject.
  - Your Needle may be blocked. Put on a new Needle and prime the Pen.
  - You may have dust, food, or liquid inside the Pen. Throw the Pen away and get a new Pen.

If you have any questions or problems with your HUMALOG Tempo Pen, contact Lilly at 1-800-LillyRx (1-800-545-5979) or call your healthcare provider for help. For more information on HUMALOG Tempo Pen and insulin, go to www.humalog.com.

Manufactured by:
Eli Lilly and Company
Indianapolis, IN 46285, USA
US License Number 1891

This Instructions for Use has been approved by the U.S. Food and Drug Administraion.

Revised: 05/2025

Scan this code to launch (www.humalog.com)

HUMALOG® is a registered trademark and HUMALOG Tempo PenTM is a trademark of Eli Lilly and Company.

Copyright © 2025, Eli Lilly and Company. All rights reserved.

HUMALOG Tempo Pen meets the current dose accuracy and functional requirements of ISO 11608-1.

LOGTP200-0001-IFU-20250507

PACKAGE CARTON – HUMALOG 10 mL vial

NDC 0002-7510-01

Humalog®

(insulin lispro)
injection

100 units per mL (U-100)

For subcutaneous or intravenous use

10 mL multiple-dose vial

Use only with a U-100 syringe

Rx only

www.humalog.com

Lilly

PACKAGE CARTON – HUMALOG 3 mL vial

NDC 0002-7533-01

Humalog®

(insulin lispro)
injection

100 units per mL (U-100)

For subcutaneous or intravenous use

3 mL multiple-dose vial

Use only with a U-100 syringe

Rx only

www.humalog.com

Lilly

PACKAGE CARTON – HUMALOG KwikPen

NDC 0002-8799-59

Humalog KwikPen®

(insulin lispro)
injection

For Single Patient Use Only

Dispense in this sealed carton.

Needles not included

100 units per mL (U-100)

This device is recommended for use with Becton, Dickinson and Company's insulin pen needles

For subcutaneous use only.

prefilled insulin delivery device

Rx only

5 x 3 mL Prefilled Pens

Read Insulin Delivery Device Instructions for Use

PACKAGE CARTON – HUMALOG Cartridge 3mL

NDC 0002-7516-59

Rx only

5 x 3 mL Cartridges

Humalog®

(insulin lispro)
injection

For Single Patient Use Only

100 units per mL (U-100)

For subcutaneous use only.

For use in Eli Lilly and Company's HumaPen® LUXURA® HD insulin delivery device.

www.humalog.com

Lilly

PACKAGE CARTON – HUMALOG Junior KwikPen

Dispense in this sealed carton.

NDC 0002-7714-59

Humalog®

Junior KwikPen®

(insulin lispro)
injection

For Single Patient Use Only

100 units per mL (U-100)

The pen can deliver 0.5 (½) to 30 units in one injection.

5 x 3 mL prefilled pens

For subcutaneous use only.

prefilled insulin delivery device

Rx only

Read Humalog® Junior KwikPen® Instructions for Use.

NEEDLES NOT INCLUDED

This device is recommended for use with Becton, Dickinson and Company's insulin pen needles.

Lilly

PACKAGE CARTON – HUMALOG Tempo Pen

NDC 0002-8213-05

Humalog®

Tempo PenTM

(insulin lispro)
injection

For Single Patient Use Only

Dispense in this sealed carton.

Needles not included

100 units per mL (U-100)

This device is recommended for use with Becton, Dickinson and Company's insulin pen needles

For subcutaneous use only.

prefilled insulin delivery device

Rx only

5 x 3 mL Prefilled Pens

Read Insulin Delivery Device Instructions for Use

PACKAGE CARTON – STERILE DILUENT Vial 10mL 1ct

1–ND 800

Lilly

10 mL

STERILE DILUENT
FOR

HUMALOG® U-100

insulin lispro injection

HUMULIN® R U-100

REGULAR insulin human injection

Insulin Lispro Injection U-100

WARNING: Use ONLY with insulins listed on side panel.

PACKAGE CARTON – HUMALOG U200 KwikPen 2ct

Dispense in this sealed carton.

NDC 0002-7712-27

Humalog KwikPen®

(insulin lispro)
injection

For Single Patient Use Only

200 units per mL (U-200)

2 x 3 mL Prefilled Pens

For subcutaneous use only.

prefilled insulin delivery device

Rx only

Read Insulin Delivery Device Instructions for Use.

NEEDLES NOT INCLUDED

This device is recommended for use with Becton, Dickinson and Company's insulin pen needles.

DO NOT TRANSFER TO A SYRINGE SEVERE OVERDOSE CAN RESULT

PACKAGE CARTON – HUMALOG U-200 Tempo Pen

Dispense in this sealed carton.

NDC 0002-8208-27

Humalog® Tempo PenTM

insulin lispro injection

For Single Patient Use Only

200 units per mL (U-200)

prefilled insulin delivery device

2 x 3 mL Prefilled Pens

Rx Only

For subcutaneous use.

Read Insulin Delivery Device Instructions for Use.

NEEDLES NOT INCLUDED

This device is recommended for use with Becton, Dickinson and Company's insulin pen needles.

DO NOT TRANSFER TO A SYRINGE SEVERE OVERDOSE CAN RESULT